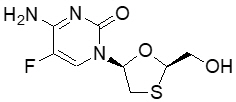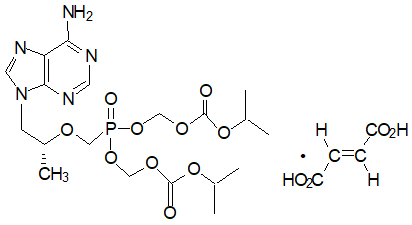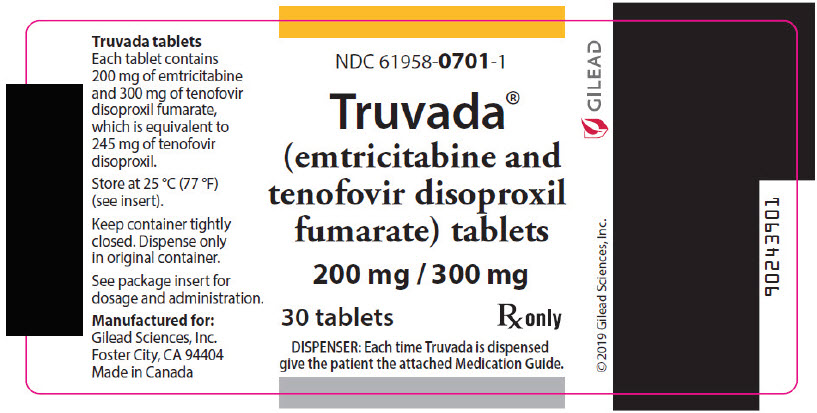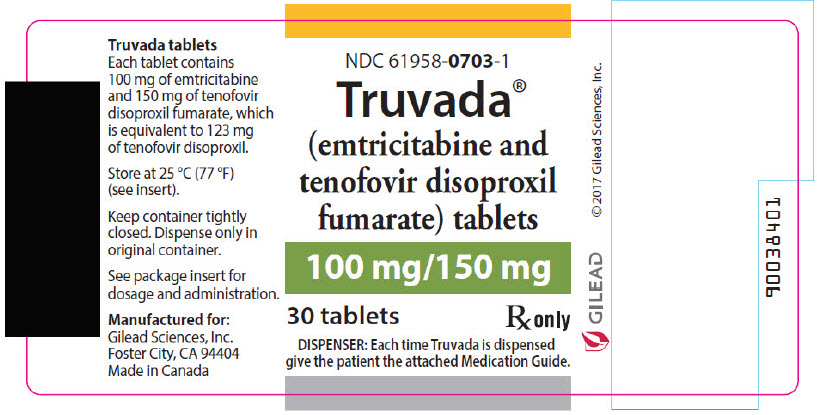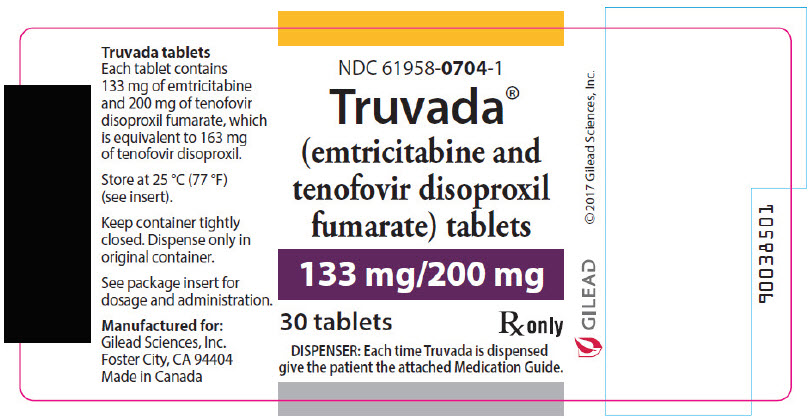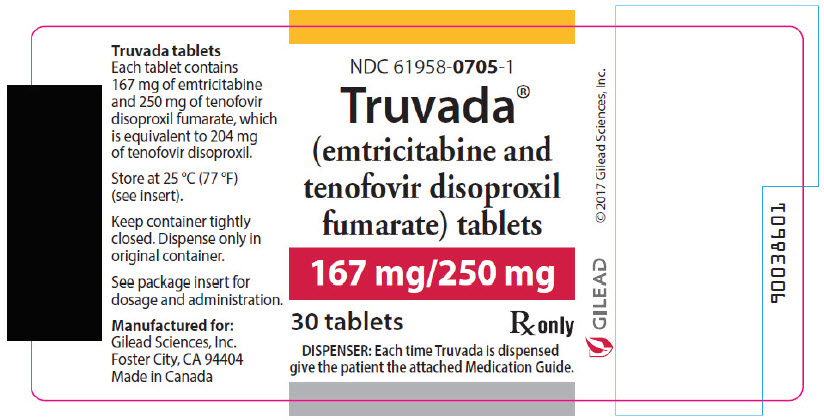 DRUG LABEL: Truvada
NDC: 61958-0701 | Form: TABLET, FILM COATED
Manufacturer: Gilead Sciences, Inc
Category: prescription | Type: HUMAN PRESCRIPTION DRUG LABEL
Date: 20250716

ACTIVE INGREDIENTS: emtricitabine 200 mg/1 1; tenofovir disoproxil fumarate 300 mg/1 1
INACTIVE INGREDIENTS: croscarmellose sodium; lactose monohydrate; magnesium stearate; microcrystalline cellulose; starch, corn; water; FD&C Blue No. 2; aluminum oxide; hypromellose, unspecified; titanium dioxide; triacetin

HIGHLIGHTS OF PRESCRIBING INFORMATION

These highlights do not include all the information needed to use TRUVADA safely and effectively. See full prescribing information for TRUVADA.
TRUVADA® (emtricitabine and tenofovir disoproxil fumarate) tablets, for oral use
Initial U.S. Approval: 2004

WARNING: POSTTREATMENT ACUTE EXACERBATION OF HEPATITIS B and RISK OF DRUG RESISTANCE WITH USE OF TRUVADA FOR HIV-1 PRE-EXPOSURE PROPHYLAXIS (PrEP) IN UNDIAGNOSED EARLY HIV-1 INFECTION

See full prescribing information for complete boxed warning.

- Severe acute exacerbations of hepatitis B (HBV) have been reported in HBV-infected individuals who have discontinued TRUVADA. Hepatic function should be monitored closely in these individuals who discontinue TRUVADA. If appropriate anti-hepatitis B therapy may be warranted. (5.1)
- TRUVADA used for HIV-1 PrEP must only be prescribed to individuals confirmed to be HIV-negative immediately prior to initiating and at least every 3 months during use. Drug-resistant HIV-1 variants have been identified with the use of TRUVADA for HIV-1 PrEP following undetected acute HIV-1 infection. Do not initiate TRUVADA for HIV-1 PrEP if signs or symptoms of acute HIV infection are present unless negative infection status is confirmed. (5.2)

1 INDICATIONS AND USAGE

HIV-1 Treatment (1.1)

TRUVADA is a two-drug combination of emtricitabine (FTC) and tenofovir disoproxil fumarate (TDF), both HIV-1 nucleoside analog reverse transcriptase inhibitors, and is indicated:

- in combination with other antiretroviral agents for the treatment of HIV-1 infection in adults and pediatric patients weighing at least 17 kg.

HIV-1 PrEP (1.2):

- TRUVADA is indicated in at-risk adults and adolescents weighing at least 35 kg for pre-exposure prophylaxis (PrEP) to reduce the risk of sexually acquired HIV-1 infection. Individuals must have a negative HIV-1 test immediately prior to initiating TRUVADA for HIV-1 PrEP.

2 DOSAGE AND ADMINISTRATION

- Testing: Prior to or when initiating TRUVADA test for hepatitis B virus infection. Prior to initiation and during use of TRUVADA, on a clinically appropriate schedule, assess serum creatinine, estimated creatinine clearance, urine glucose, and urine protein in all individuals. In individuals with chronic kidney disease, also assess serum phosphorus. (2.1)
- HIV-1 Screening: Screen all individuals for HIV-1 infection immediately prior to initiating TRUVADA for HIV-1 PrEP and at least once every 3 months while taking TRUVADA, and upon diagnosis of any other sexually transmitted infections (STIs). (2.2)

Treatment of HIV-1 Infection

- Recommended dosage in adults and pediatric patients weighing at least 35 kg: One TRUVADA tablet (containing 200 mg of FTC and 300 mg of TDF) once daily taken orally with or without food. (2.3)
- Recommended dosage in pediatric patients weighing at least 17 kg: One TRUVADA low-strength tablet (100 mg/150 mg, 133 mg/200 mg, or 167 mg/250 mg based on body weight) once daily taken orally with or without food. (2.4)
- Recommended dosage in renally impaired HIV-1 infected adult patients:
  - Creatinine clearance (CrCl) 30−49 mL/min: 1 tablet every 48 hours. (2.6)
  - CrCl below 30 mL/min or hemodialysis: TRUVADA is not recommended. (2.6)

HIV-1 Pre-Exposure Prophylaxis (PrEP)

- Recommended dosage in HIV-1 uninfected adults and adolescents weighing at least 35 kg: One TRUVADA tablet (containing 200 mg of FTC and 300 mg of TDF) once daily taken orally with or without food. (2.5)
- Recommended dosage in renally impaired HIV-uninfected individuals: TRUVADA is not recommended in HIV-uninfected individuals if CrCl is below 60 mL/min. (2.6)

3 DOSAGE FORMS AND STRENGTHS

Tablets: 200 mg/300 mg, 167 mg/250 mg, 133 mg/200 mg, and 100 mg/150 mg of emtricitabine and tenofovir disoproxil fumarate, respectively. (3)

4 CONTRAINDICATIONS

TRUVADA for HIV-1 PrEP is contraindicated in individuals with unknown or positive HIV-1 status. (4)

5 WARNINGS AND PRECAUTIONS

- Comprehensive management to reduce the risk of acquiring HIV-1 when TRUVADA is used for HIV-1 PrEP: Use as part of a comprehensive prevention strategy including other prevention measures; strictly adhere to dosing schedule. (5.2)
- Management to reduce the risk of acquiring HIV-1 drug resistance when TRUVADA is used for HIV-1 PrEP: refer to full prescribing information for additional detail. (5.2)
- New onset or worsening renal impairment: Can include acute renal failure and Fanconi syndrome. Avoid administering TRUVADA with concurrent or recent use of nephrotoxic drugs. (5.3)
- Immune reconstitution syndrome during treatment of HIV-1 infection: May necessitate further evaluation and treatment. (5.4)
- Decreases in bone mineral density (BMD): Consider assessment of BMD in individuals with a history of pathologic fracture or other risk factors for osteoporosis or bone loss. (5.5)
- Lactic acidosis/severe hepatomegaly with steatosis: Discontinue TRUVADA in individuals who develop symptoms or laboratory findings suggestive of lactic acidosis or pronounced hepatotoxicity. (5.6)

6 ADVERSE REACTIONS

- In HIV-1 infected patients, the most common adverse reactions (incidence greater than or equal to 10%) are diarrhea, nausea, fatigue, headache, dizziness, depression, insomnia, abnormal dreams, and rash. (6.1)
- In HIV-1 uninfected adults in PrEP trials, adverse reactions that were reported by more than 2% of TRUVADA participants and more frequently than by placebo participants were headache, abdominal pain, and weight decreased. (6.1)

To report SUSPECTED ADVERSE REACTIONS, contact Gilead Sciences, Inc. at 1-800-445-3235 or FDA at 1-800-FDA-1088 or www.fda.gov/medwatch

7 DRUG INTERACTIONS

- Tenofovir disoproxil fumarate increases didanosine concentrations. Dose reduction and close monitoring for didanosine toxicity are warranted. (7.2)
- Coadministration decreases atazanavir concentrations. When coadministered with TRUVADA, use atazanavir given with ritonavir. (7.2)
- Coadministration of TRUVADA with certain HIV-1 protease inhibitors or certain drugs to treat HCV increases tenofovir concentrations. Monitor for evidence of tenofovir toxicity. (7.2)
- Consult Full Prescribing Information prior to and during treatment for important drug interactions. (7.2)

8 USE IN SPECIFIC POPULATIONS

Lactation: Mothers infected with HIV-1 or suspected of having acquired HIV-1 infection should be instructed not to breastfeed due to the potential for HIV transmission. (8.2)

FULL PRESCRIBING INFORMATION

WARNING: POSTTREATMENT ACUTE EXACERBATION OF HEPATITIS B and RISK OF DRUG RESISTANCE WITH USE OF TRUVADA FOR HIV-1 PRE-EXPOSURE PROPHYLAXIS (PrEP) IN UNDIAGNOSED EARLY HIV-1 INFECTION

Severe acute exacerbations of hepatitis B (HBV) have been reported in HBV-infected individuals who have discontinued TRUVADA. Hepatic function should be monitored closely with both clinical and laboratory follow-up for at least several months in individuals who are infected with HBV and discontinue TRUVADA. If appropriate, anti-hepatitis B therapy may be warranted [see Warnings and Precautions (5.1)].

TRUVADA used for HIV-1 PrEP must only be prescribed to individuals confirmed to be HIV-negative immediately prior to initiating and at least every 3 months during use. Drug-resistant HIV-1 variants have been identified with use of TRUVADA for HIV-1 PrEP following undetected acute HIV-1 infection. Do not initiate TRUVADA for HIV-1 PrEP if signs or symptoms of acute HIV-1 infection are present unless negative infection status is confirmed [see Warnings and Precautions (5.2)].

1 INDICATIONS AND USAGE

1.1 Treatment of HIV-1 Infection

TRUVADA is indicated in combination with other antiretroviral agents for the treatment of HIV-1 infection in adults and pediatric patients weighing at least 17 kg [see Clinical Studies (14)].

1.2 HIV-1 Pre-Exposure Prophylaxis (PrEP)

TRUVADA is indicated in at-risk adults and adolescents weighing at least 35 kg for pre-exposure prophylaxis (PrEP) to reduce the risk of sexually acquired HIV-1 infection. Individuals must have a negative HIV-1 test immediately prior to initiating TRUVADA for HIV-1 PrEP [see Dosage and Administration (2.2), Warnings and Precautions (5.2)].

2 DOSAGE AND ADMINISTRATION

2.1 Testing Prior to Initiation of TRUVADA for Treatment of HIV-1 Infection or for HIV-1 PrEP

Prior to or when initiating TRUVADA, test individuals for hepatitis B virus infection [see Warnings and Precautions (5.1)].

Prior to initiation, and during use of TRUVADA, on a clinically appropriate schedule, assess serum creatinine, estimated creatinine clearance, urine glucose, and urine protein in all individuals. In individuals with chronic kidney disease, also assess serum phosphorus [see Warnings and Precautions (5.3)].

2.2 HIV-1 Screening for Individuals Receiving TRUVADA for HIV-1 PrEP

Screen all individuals for HIV-1 infection immediately prior to initiating TRUVADA for HIV-1 PrEP and at least once every 3 months while taking TRUVADA, and upon diagnosis of any other sexually transmitted infections (STIs) [see Indications and Usage (1.2), Contraindications (4), and Warnings and Precautions (5.2)].

If recent (<1 month) exposures to HIV-1 are suspected or clinical symptoms consistent with acute HIV-1 infection are present, use a test approved or cleared by the FDA as an aid in the diagnosis of acute or primary HIV-1 infection [see Warnings and Precautions (5.2), Use in Specific Populations (8.4), and Clinical Studies (14.3 and 14.4)].

2.3 Recommended Dosage for Treatment of HIV-1 Infection in Adults and Pediatric Patients Weighing at Least 35 kg

TRUVADA is a two-drug fixed dose combination product containing emtricitabine (FTC) and tenofovir disoproxil fumarate (TDF). The recommended dosage of TRUVADA in adults and in pediatric patients weighing at least 35 kg is one tablet (containing 200 mg of FTC and 300 mg of TDF) once daily taken orally with or without food [see Clinical Pharmacology (12.3)].

2.4 Recommended Dosage for Treatment of HIV-1 Infection in Pediatric Patients Weighing at Least 17 kg and Able to Swallow a Tablet

The recommended oral dosage of TRUVADA for pediatric patients weighing at least 17 kg and who can swallow a tablet is presented in Table 1. Tablets should be taken once daily with or without food. Weight should be monitored periodically and the TRUVADA dose adjusted accordingly.

Table 1 Dosing for Treatment of HIV-1 Infection in Pediatric Patients Weighing 17 kg to less than 35 kg
Body Weight (kg) | Dosing of TRUVADA (FTC/TDF)
17 to less than 22 | one 100 mg /150 mg tablet once daily
22 to less than 28 | one 133 mg /200 mg tablet once daily
28 to less than 35 | one 167 mg /250 mg tablet once daily

2.5 Recommended Dosage for HIV-1 PrEP in Adults and Adolescents Weighing at Least 35 kg

The dosage of TRUVADA for HIV-1 PrEP is one tablet (containing 200 mg of FTC and 300 mg of TDF) once daily taken orally with or without food in HIV-1 uninfected adults and adolescents weighing at least 35 kg [see Clinical Pharmacology (12.3)].

2.6 Dosage Adjustment in Individuals with Renal Impairment

Treatment of HIV-1 Infection

Table 2 provides dosage interval adjustment for patients with renal impairment. No dosage adjustment is necessary for HIV-1 infected patients with mild renal impairment (creatinine clearance 50–80 mL/min). The safety and effectiveness of the dosing interval adjustment recommendations in patients with moderate renal impairment (creatinine clearance 30–49 mL/min) have not been clinically evaluated; therefore, clinical response to treatment and renal function should be closely monitored in these patients [see Warnings and Precautions (5.3)].

No data are available to make dosage recommendations in pediatric patients with renal impairment.

Table 2 Dosage Interval Adjustment for HIV-1 Infected Adult Patients with Altered Creatinine Clearance
 | Creatinine Clearance (mL/min) [Calculated using ideal (lean) body weight]
 | ≥50 | 30–49 | <30 (Including Patients Requiring Hemodialysis)
Recommended Dosing Interval | Every 24 hours | Every 48 hours | TRUVADA is not recommended.

HIV-1 PrEP

TRUVADA for HIV-1 PrEP is not recommended in HIV-1 uninfected individuals with estimated creatinine clearance below 60 mL/min [see Warnings and Precautions (5.3)].

If a decrease in estimated creatinine clearance is observed in uninfected individuals while using TRUVADA for HIV-1 PrEP, evaluate potential causes and re-assess potential risks and benefits of continued use [see Warnings and Precautions (5.3)].

3 DOSAGE FORMS AND STRENGTHS

TRUVADA tablets are available in four dose strengths.

- 100 mg/150 mg Tablets: 100 mg of emtricitabine (FTC) and 150 mg of tenofovir disoproxil fumarate (TDF) (equivalent to 123 mg of tenofovir disoproxil): blue, oval shaped, film coated, debossed with "GSI" on one side and with "703" on the other side.
- 133 mg/200 mg Tablets: 133 mg of FTC and 200 mg of TDF (equivalent to 163 mg of tenofovir disoproxil): blue, rectangular shaped, film coated, debossed with "GSI" on one side and with "704" on the other side.
- 167 mg/250 mg Tablets: 167 mg of FTC and 250 mg of TDF (equivalent to 204 mg of tenofovir disoproxil): blue, modified capsule shaped, film coated, debossed with "GSI" on one side and with "705" on the other side.
- 200 mg/300 mg Tablets: 200 mg of FTC and 300 mg of TDF (equivalent to 245 mg of tenofovir disoproxil): blue, capsule shaped, film coated, debossed with "GILEAD" on one side and with "701" on the other side.

4 CONTRAINDICATIONS

TRUVADA for HIV-1 PrEP is contraindicated in individuals with unknown or positive HIV-1 status [see Warnings and Precautions (5.2)].

5 WARNINGS AND PRECAUTIONS

5.1 Severe Acute Exacerbation of Hepatitis B in Individuals with HBV Infection

All individuals should be tested for the presence of chronic hepatitis B virus (HBV) before or when initiating TRUVADA [see Dosage and Administration (2.1)].

Severe acute exacerbations of hepatitis B (e.g., liver decompensation and liver failure) have been reported in HBV-infected individuals who have discontinued TRUVADA. Individuals infected with HBV who discontinue TRUVADA should be closely monitored with both clinical and laboratory follow-up for at least several months after stopping treatment. If appropriate, anti-hepatitis B therapy may be warranted, especially in individuals with advanced liver disease or cirrhosis, since posttreatment exacerbation of hepatitis may lead to hepatic decompensation and liver failure. HBV-uninfected individuals should be offered vaccination.

5.2 Comprehensive Management to Reduce the Risk of Sexually Transmitted Infections, Including HIV-1, and Development of HIV-1 Resistance When TRUVADA Is Used for HIV-1 PrEP

Use TRUVADA for HIV-1 PrEP to reduce the risk of HIV-1 infection as part of a comprehensive prevention strategy that includes other prevention measures, including adherence to daily administration and safer sex practices, including condoms, to reduce the risk of sexually transmitted infections (STIs). The time from initiation of TRUVADA for HIV-1 PrEP to maximal protection against HIV-1 infection is unknown.

Risk for HIV-1 acquisition includes behavioral, biological, or epidemiologic factors including but not limited to condomless sex, past or current STIs, self-identified HIV risk, having sexual partners of unknown HIV-1 viremic status, or sexual activity in a high prevalence area or network.

Counsel individuals on the use of other prevention measures (e.g., consistent and correct condom use, knowledge of partner(s)' HIV-1 status, including viral suppression status, regular testing for STIs that can facilitate HIV-1 transmission). Inform uninfected individuals about and support their efforts in reducing sexual risk behavior.

Use TRUVADA to reduce the risk of acquiring HIV-1 only in individuals confirmed to be HIV-negative. HIV-1 resistance substitutions may emerge in individuals with undetected HIV-1 infection who are taking only TRUVADA, because TRUVADA alone does not constitute a complete regimen for HIV-1 treatment [see Microbiology (12.4)]; therefore, care should be taken to minimize the risk of initiating or continuing TRUVADA before confirming the individual is HIV-1 negative.

- Some HIV-1 tests only detect anti-HIV antibodies and may not identify HIV-1 during the acute stage of infection. Prior to initiating TRUVADA for HIV-1 PrEP, ask seronegative individuals about recent (in past month) potential exposure events (e.g., condomless sex or condom breaking during sex with a partner of unknown HIV-1 status or unknown viremic status, or a recent STI), and evaluate for current or recent signs or symptoms consistent with acute HIV-1 infection (e.g., fever, fatigue, myalgia, skin rash).
- If recent (<1 month) exposures to HIV-1 are suspected or clinical symptoms consistent with acute HIV-1 infection are present, use a test approved or cleared by the FDA as an aid in the diagnosis of acute or primary HIV-1 infection.

While using TRUVADA for HIV-1 PrEP, HIV-1 testing should be repeated at least every 3 months, and upon diagnosis of any other STIs.

- If an HIV-1 test indicates possible HIV-1 infection, or if symptoms consistent with acute HIV-1 infection develop following a potential exposure event, convert the HIV-1 PrEP regimen to an HIV treatment regimen until negative infection status is confirmed using a test approved or cleared by the FDA as an aid in the diagnosis of acute or primary HIV-1 infection.

Counsel HIV-1 uninfected individuals to strictly adhere to the once daily TRUVADA dosing schedule. The effectiveness of TRUVADA in reducing the risk of acquiring HIV-1 is strongly correlated with adherence, as demonstrated by measurable drug levels in clinical trials of TRUVADA for HIV-1 PrEP. Some individuals, such as adolescents, may benefit from more frequent visits and counseling to support adherence [see Use in Specific Populations (8.4), Microbiology (12.4), and Clinical Studies (14.3 and 14.4)].

5.3 New Onset or Worsening Renal Impairment

Emtricitabine and tenofovir are principally eliminated by the kidney. Renal impairment, including cases of acute renal failure and Fanconi syndrome (renal tubular injury with severe hypophosphatemia), has been reported with the use of TDF, a component of TRUVADA [see Adverse Reactions (6.2)].

Prior to initiation and during use of TRUVADA, on a clinically appropriate schedule, assess serum creatinine, estimated creatinine clearance, urine glucose, and urine protein in all individuals. In individuals with chronic kidney disease, also assess serum phosphorus.

TRUVADA should be avoided with concurrent or recent use of a nephrotoxic agent (e.g., high-dose or multiple non-steroidal anti-inflammatory drugs [NSAIDs]) [see Drug Interactions (7.1)]. Cases of acute renal failure after initiation of high-dose or multiple NSAIDs have been reported in HIV-infected patients with risk factors for renal dysfunction who appeared stable on TDF. Some patients required hospitalization and renal replacement therapy. Alternatives to NSAIDs should be considered, if needed, in patients at risk for renal dysfunction.

Persistent or worsening bone pain, pain in extremities, fractures, and/or muscular pain or weakness may be manifestations of proximal renal tubulopathy and should prompt an evaluation of renal function in individuals at risk of renal dysfunction.

Treatment of HIV-1 Infection

Dosing interval adjustment of TRUVADA and close monitoring of renal function are recommended in all patients with estimated creatinine clearance 30–49 mL/min [see Dosage and Administration (2.6)]. No safety or efficacy data are available in patients with renal impairment who received TRUVADA using these dosing guidelines, so the potential benefit of TRUVADA therapy should be assessed against the potential risk of renal toxicity. TRUVADA is not recommended in patients with estimated creatinine clearance below 30 mL/min or patients requiring hemodialysis.

HIV-1 PrEP

TRUVADA for HIV-1 PrEP is not recommended in uninfected individuals with estimated creatinine clearance less than 60 mL/min. If a decrease in estimated creatinine clearance is observed while using TRUVADA for HIV-1 PrEP, evaluate potential causes and re-assess potential risks and benefits of continued use [see Dosage and Administration (2.6)].

5.4 Immune Reconstitution Syndrome

Immune reconstitution syndrome has been reported in HIV-1 infected patients treated with combination antiretroviral therapy, including TRUVADA. During the initial phase of combination antiretroviral treatment, HIV-1 infected patients whose immune system responds may develop an inflammatory response to indolent or residual opportunistic infections (such as Mycobacterium avium infection, cytomegalovirus, Pneumocystis jirovecii pneumonia [PCP], or tuberculosis), which may necessitate further evaluation and treatment.

Autoimmune disorders (such as Graves' disease, polymyositis, Guillain-Barré syndrome, and autoimmune hepatitis) have also been reported to occur in the setting of immune reconstitution; however, the time to onset is more variable and can occur many months after initiation of treatment.

5.5 Bone Loss and Mineralization Defects

Bone Mineral Density

In clinical trials in HIV-1 infected adults and in a clinical trial of HIV-1 uninfected individuals, TDF (a component of TRUVADA) was associated with slightly greater decreases in bone mineral density (BMD) and increases in biochemical markers of bone metabolism, suggesting increased bone turnover relative to comparators [see Adverse Reactions (6.1)]. Serum parathyroid hormone levels and 1,25 Vitamin D levels were also higher in subjects receiving TDF.

Clinical trials evaluating TDF in pediatric and adolescent subjects were conducted. Under normal circumstances, BMD increases rapidly in pediatric patients. In HIV-1 infected subjects aged 2 years to less than 18 years, bone effects were similar to those observed in adult subjects and suggest increased bone turnover. Total body BMD gain was less in the TDF-treated HIV-1 infected pediatric subjects as compared to the control groups. Similar trends were observed in adolescent subjects aged 12 years to less than 18 years treated for chronic hepatitis B. In all pediatric trials, skeletal growth (height) appeared to be unaffected.

The effects of TDF-associated changes in BMD and biochemical markers on long-term bone health and future fracture risk are unknown. Assessment of BMD should be considered for adult and pediatric patients who have a history of pathologic bone fracture or other risk factors for osteoporosis or bone loss. Although the effect of supplementation with calcium and vitamin D was not studied, such supplementation may be beneficial. If bone abnormalities are suspected, appropriate consultation should be obtained.

Mineralization Defects

Cases of osteomalacia associated with proximal renal tubulopathy, manifested as bone pain or pain in extremities and which may contribute to fractures, have been reported in association with TDF use [see Adverse Reactions (6.1)]. Arthralgia and muscle pain or weakness have also been reported in cases of proximal renal tubulopathy. Hypophosphatemia and osteomalacia secondary to proximal renal tubulopathy should be considered in patients at risk of renal dysfunction who present with persistent or worsening bone or muscle symptoms while receiving TDF-containing products [see Warnings and Precautions (5.3)].

5.6 Lactic Acidosis/Severe Hepatomegaly with Steatosis

Lactic acidosis and severe hepatomegaly with steatosis, including fatal cases, have been reported with the use of nucleoside analogs, including FTC and TDF, components of TRUVADA, alone or in combination with other antiretrovirals. Treatment with TRUVADA should be suspended in any individual who develops clinical or laboratory findings suggestive of lactic acidosis or pronounced hepatotoxicity (which may include hepatomegaly and steatosis even in the absence of marked transaminase elevations).

5.7 Risk of Adverse Reactions Due to Drug Interactions

The concomitant use of TRUVADA and other drugs may result in known or potentially significant drug interactions, some of which may lead to possible clinically significant adverse reactions from greater exposures of concomitant drugs [see Drug Interactions (7.2)].

See Table 7 for steps to prevent or manage these possible and known significant drug interactions, including dosing recommendations. Consider the potential for drug interactions prior to and during therapy with TRUVADA; review concomitant medications during therapy with TRUVADA; and monitor for adverse reactions associated with the concomitant drugs.

6 ADVERSE REACTIONS

The following adverse reactions are discussed in other sections of the labeling:

- Severe Acute Exacerbations of Hepatitis B in Patients with HBV Infection [see Warnings and Precautions (5.1)].
- New Onset or Worsening Renal Impairment [see Warnings and Precautions (5.3)].
- Immune Reconstitution Syndrome [see Warnings and Precautions (5.4)].
- Bone Loss and Mineralization Defects [see Warnings and Precautions (5.5)].
- Lactic Acidosis/Severe Hepatomegaly with Steatosis [see Warnings and Precautions (5.6)].

6.1 Clinical Trials Experience

Because clinical trials are conducted under widely varying conditions, adverse reaction rates observed in the clinical trials of a drug cannot be directly compared to rates in the clinical trials of another drug and may not reflect the rates observed in practice.

Adverse Reactions from Clinical Trials Experience in HIV-1 Infected Subjects

Clinical Trials in Adult Subjects

In Study 934, 511 antiretroviral-naïve subjects received efavirenz (EFV) administered in combination with either FTC+TDF (N=257) or zidovudine (AZT)/lamivudine (3TC) (N=254) for 144 weeks. The most common adverse reactions (incidence greater than or equal to 10%, all grades) included diarrhea, nausea, fatigue, headache, dizziness, depression, insomnia, abnormal dreams, and rash. Table 3 provides the treatment-emergent adverse reactions (Grades 2–4) occurring in greater than or equal to 5% of subjects treated in any treatment group.

Skin discoloration, manifested by hyperpigmentation, occurred in 3% of subjects taking FTC+TDF, and was generally mild and asymptomatic. The mechanism and clinical significance are unknown.

Table 3 Selected Adverse Reactions [Frequencies of adverse reactions are based on all treatment-emergent adverse events, regardless of relationship to study drug.] (Grades 2–4) Reported in ≥5% in Any Treatment Group in Study 934 (0–144 Weeks)
 | FTC+TDF+EFV [From Weeks 96 to 144 of the trial, subjects received TRUVADA with efavirenz in place of FTC+TDF with efavirenz.] | AZT/3TC+EFV
 | N=257 | N=254
Fatigue | 9% | 8%
Depression | 9% | 7%
Nausea | 9% | 7%
Diarrhea | 9% | 5%
Dizziness | 8% | 7%
Upper respiratory tract infections | 8% | 5%
Sinusitis | 8% | 4%
Rash event [Rash event includes rash, exfoliative rash, rash generalized, rash macular, rash maculo-papular, rash pruritic, and rash vesicular.] | 7% | 9%
Headache | 6% | 5%
Insomnia | 5% | 7%
Nasopharyngitis | 5% | 3%
Vomiting | 2% | 5%

Laboratory Abnormalities: Laboratory abnormalities observed in this trial were generally consistent with those seen in other trials of TDF and/or FTC (Table 4).

Table 4 Significant Laboratory Abnormalities Reported in ≥1% of Subjects in Any Treatment Group in Study 934 (0–144 Weeks)
 | FTC+TDF+EFV [From Weeks 96 to 144 of the trial, subjects received TRUVADA with efavirenz in place of FTC+TDF with efavirenz.] | AZT/3TC+EFV
 | N=257 | N=254
Any ≥ Grade 3 Laboratory Abnormality | 30% | 26%
Fasting Cholesterol (>240 mg/dL) | 22% | 24%
Creatine Kinase (M: >990 U/L) (F: >845 U/L) | 9% | 7%
Serum Amylase (>175 U/L) | 8% | 4%
Alkaline Phosphatase (>550 U/L) | 1% | 0%
AST (M: >180 U/L) (F: >170 U/L) | 3% | 3%
ALT (M: >215 U/L) (F: >170 U/L) | 2% | 3%
Hemoglobin (<8.0 mg/dL) | 0% | 4%
Hyperglycemia (>250 mg/dL) | 2% | 1%
Hematuria (>75 RBC/HPF) | 3% | 2%
Glycosuria (≥3+) | <1% | 1%
Neutrophils (<750/mm^3) | 3% | 5%
Fasting Triglycerides (>750 mg/dL) | 4% | 2%

Clinical Trials in Pediatric Subjects

Emtricitabine: In addition to the adverse reactions reported in adults, anemia and hyperpigmentation were observed in 7% and 32%, respectively, of pediatric subjects (3 months to less than 18 years of age) who received treatment with FTC in the larger of two open-label, uncontrolled pediatric trials (N=116).

Tenofovir Disoproxil Fumarate: In pediatric clinical trials (Studies 352 and 321) conducted in 184 HIV-1 infected subjects 2 to less than 18 years of age, the adverse reactions observed in pediatric subjects who received treatment with TDF were consistent with those observed in clinical trials of TDF in adults.

In Study 352 (2 to less than 12 years of age), 89 pediatric subjects received TDF for a median exposure of 104 weeks. Of these, 4 subjects discontinued from the trial due to adverse reactions consistent with proximal renal tubulopathy. Three of these 4 subjects presented with hypophosphatemia and had decreases in total body or spine BMD Z-score [see Warnings and Precautions (5.5)]. Total body BMD gain at Week 48 was less in the TDF group compared to the stavudine (d4T) or zidovudine (AZT) treatment groups. The mean rate of BMD gain in lumbar spine was similar between treatment groups. One TDF-treated subject and none of the d4T- or AZT-treated subjects experienced significant (greater than 4%) lumbar spine BMD loss at Week 48. Changes from baseline in BMD Z-scores were −0.012 for lumbar spine and −0.338 for total body in the 64 subjects who were treated with TDF for 96 weeks.

In Study 321 (12 to less than 18 years of age), the mean rate of BMD gain at Week 48 was less in the TDF compared to the placebo treatment group. Six TDF-treated subjects and one placebo-treated subject had significant (greater than 4%) lumbar spine BMD loss at Week 48. Changes from baseline BMD Z-scores were −0.341 for lumbar spine and −0.458 for total body in the 28 subjects who were treated with TDF for 96 weeks.

In both trials, skeletal growth (height) appeared to be unaffected.

Adverse Reactions from Clinical Trial Experience in Uninfected Subjects Taking TRUVADA for HIV-1 PrEP

Clinical Trials in Adult Subjects

The safety profile of TRUVADA for HIV-1 PrEP was comparable to that observed in clinical trials of HIV-infected subjects based on two randomized placebo-controlled clinical trials (iPrEx, Partners PrEP) in which 2,830 HIV-1 uninfected adults received TRUVADA once daily for HIV-1 PrEP. Subjects were followed for a median of 71 weeks and 87 weeks, respectively. Table 5 provides a list of selected adverse events that occurred in 2% or more of subjects in any treatment group in the iPrEx trial, with an incidence greater than placebo.

Table 5 Selected Adverse Events (All Grades) Reported in ≥2% in Any Treatment Group in the iPrEx Trial and Greater than Placebo
 | FTC/TDF (N=1251) | Placebo (N=1248)
Headache | 7% | 6%
Abdominal pain | 4% | 2%
Weight decreased | 3% | 2%

In the Partners PrEP trial, the frequency of adverse events in the TRUVADA treatment group was generally either less than or the same as in the placebo group.

Laboratory Abnormalities: Table 6 provides a list of Grade 2–4 laboratory abnormalities observed in the iPrEx and Partners PrEP trials. Six subjects in the TDF-containing arms of the Partners PrEP trial discontinued from the trial due to an increase in serum creatinine compared with no discontinuations in the placebo group. One subject in the TRUVADA arm of the iPrEx trial discontinued from the trial due to an increase in serum creatinine and another subject discontinued due to low serum phosphorus. Grades 2−3 proteinuria (2–4+) and/or glycosuria (3+) occurred in less than 1% of subjects treated with TRUVADA in the iPrEx trial and Partners PrEP trial.

Table 6 Laboratory Abnormalities (Highest Toxicity Grade Reported for Each Subject) in the iPrEx Trial and Partners PrEP Trial
 | iPrEx Trial |  | Partners PrEP Trial
Grade 2–4 [Grading is per DAIDS criteria.] | FTC/TDF (N=1251) | Placebo (N=1248) | FTC/TDF (N=1579) | Placebo (N=1584)
Creatinine (>1.4 × ULN) | <1% | <1% | <1% | <1%
Phosphorus (<2.0 mg/dL) | 10% | 8% | 9% | 9%
AST (>2.6 × ULN) | 5% | 5% | <1% | <1%
ALT (>2.6 × ULN) | 7% | 7% | <1% | <1%
Hemoglobin (<9.4 mg/dL) | 1% | 2% | 2% | 2%
Neutrophils (<750/mm^3) | <1% | <1% | 5% | 3%

Changes in Bone Mineral Density: In clinical trials of HIV-1 uninfected individuals, decreases in BMD were observed. In the iPrEx trial, a substudy of 503 subjects found mean changes from baseline in BMD ranging from –0.4% to –1.0% across total hip, spine, femoral neck, and trochanter in the TRUVADA group compared with the placebo group, which returned toward baseline after discontinuation of treatment. Thirteen percent of TRUVADA-treated subjects versus 6% of placebo-treated subjects lost at least 5% of BMD at the spine during treatment. Bone fractures were reported in 1.7% of the TRUVADA group compared with 1.4% in the placebo group. No correlation between BMD and fractures was noted [see Clinical Studies (14.3)]. The Partners PrEP trial found similar fracture rates between the treatment and placebo groups (0.8% and 0.6%, respectively); no BMD evaluations were performed in this trial [see Clinical Studies (14.4)].

Clinical Trials in Adolescent Subjects

In a single-arm, open-label clinical trial (ATN113), in which 67 HIV-1 uninfected adolescent (15 to 18 years of age) men who have sex with men received TRUVADA once daily for HIV-1 PrEP, the safety profile of TRUVADA was similar to that observed in adults. Median duration to exposure of TRUVADA was 47 weeks [see Use in Specific Populations (8.4)].

In the ATN113 trial, median BMD increased from baseline to Week 48, +2.58% for lumbar spine and +0.72% for total body. One subject had significant (greater than or equal to 4%) total body BMD loss at Week 24. Median changes from baseline BMD Z-scores were 0.0 for lumbar spine and −0.2 for total body at Week 48. Three subjects showed a worsening (change from > −2 to ≤ −2) from baseline in their lumbar spine or total body BMD Z-scores at Week 24 or 48. Interpretation of these data, however, may be limited by the low rate of adherence to TRUVADA by Week 48.

6.2 Postmarketing Experience

The following adverse reactions have been identified during postapproval use of TDF. No additional adverse reactions have been identified during postapproval use of FTC. Because postmarketing reactions are reported voluntarily from a population of uncertain size, it is not always possible to reliably estimate their frequency or establish a causal relationship to drug exposure.

Immune System Disorders
allergic reaction, including angioedema

Metabolism and Nutrition Disorders
lactic acidosis, hypokalemia, hypophosphatemia

Respiratory, Thoracic, and Mediastinal Disorders
dyspnea

Gastrointestinal Disorders
pancreatitis, increased amylase, abdominal pain

Hepatobiliary Disorders
hepatic steatosis, hepatitis, increased liver enzymes (most commonly AST, ALT gamma GT)

Skin and Subcutaneous Tissue Disorders
rash

Musculoskeletal and Connective Tissue Disorders
rhabdomyolysis, osteomalacia (manifested as bone pain and which may contribute to fractures), muscular weakness, myopathy

Renal and Urinary Disorders
acute renal failure, renal failure, acute tubular necrosis, Fanconi syndrome, proximal renal tubulopathy, interstitial nephritis (including acute cases), nephrogenic diabetes insipidus, renal insufficiency, increased creatinine, proteinuria, polyuria

General Disorders and Administration Site Conditions
asthenia

The following adverse reactions, listed under the body system headings above, may occur as a consequence of proximal renal tubulopathy: rhabdomyolysis, osteomalacia, hypokalemia, muscular weakness, myopathy, hypophosphatemia.

7 DRUG INTERACTIONS

7.1 Drugs Affecting Renal Function

FTC and tenofovir are primarily excreted by the kidneys by a combination of glomerular filtration and active tubular secretion [see Clinical Pharmacology (12.3)]. No drug-drug interactions due to competition for renal excretion have been observed; however, coadministration of TRUVADA with drugs that are eliminated by active tubular secretion may increase concentrations of FTC, tenofovir, and/or the coadministered drug. Some examples include, but are not limited to, acyclovir, adefovir dipivoxil, cidofovir, ganciclovir, valacyclovir, valganciclovir, aminoglycosides (e.g., gentamicin), and high-dose or multiple NSAIDs [see Warnings and Precautions (5.3)]. Drugs that decrease renal function may increase concentrations of FTC and/or tenofovir.

7.2 Established and Significant Interactions

Table 7 provides a listing of established or clinically significant drug interactions. The drug interactions described are based on studies conducted with either TRUVADA, the components of TRUVADA (FTC and TDF) as individual agents and/or in combination, or are predicted drug interactions that may occur with TRUVADA [see Clinical Pharmacology (12.3)].

Table 7 Established and Significant [This table is not all inclusive.] Drug Interactions: Alteration in Dose or Regimen May Be Recommended Based on Drug Interaction Trials
Concomitant Drug Class: Drug Name | Effect on Concentration [↑=Increase, ↓=Decrease] | Clinical Comment
NRTI: didanosine [Indicates that a drug-drug interaction trial was conducted.] | ↑ didanosine | Patients receiving TRUVADA and didanosine should be monitored closely for didanosine-associated adverse reactions. Discontinue didanosine in patients who develop didanosine-associated adverse reactions. Higher didanosine concentrations could potentiate didanosine-associated adverse reactions, including pancreatitis, and neuropathy. Suppression of CD4+ cell counts has been observed in patients receiving TDF with didanosine 400 mg daily. In patients weighing greater than 60 kg, reduce the didanosine dose to 250 mg when it is coadministered with TRUVADA. Data are not available to recommend a dose adjustment of didanosine for adult or pediatric patients weighing less than 60 kg. When coadministered, TRUVADA and Videx EC may be taken under fasted conditions or with a light meal (less than 400 kcal, 20% fat).
HIV-1 Protease Inhibitors: atazanavir | ↓ atazanavir | When coadministered with TRUVADA, atazanavir 300 mg should be given with ritonavir 100 mg.
lopinavir/ritonavir atazanavir/ritonavir darunavir/ritonavir | ↑ tenofovir | Monitor patients receiving TRUVADA concomitantly with lopinavir/ritonavir, ritonavir-boosted atazanavir, or ritonavir-boosted darunavir for TDF-associated adverse reactions. Discontinue TRUVADA in patients who develop TDF-associated adverse reactions.
Hepatitis C Antiviral Agents: sofosbuvir/velpatasvir sofosbuvir/velpatasvir/voxilaprevir | ↑ tenofovir | Monitor patients receiving TRUVADA concomitantly with EPCLUSA® (sofosbuvir/velpatasvir) or VOSEVI® (sofosbuvir/velpatasvir/voxilaprevir) for adverse reactions associated with TDF.
ledipasvir/sofosbuvir |  | Monitor patients receiving TRUVADA concomitantly with HARVONI® (ledipasvir/sofosbuvir) without an HIV-1 protease inhibitor/ritonavir or an HIV-1 protease inhibitor/cobicistat combination for adverse reactions associated with TDF. In patients receiving TRUVADA concomitantly with HARVONI and an HIV-1 protease inhibitor/ritonavir or an HIV-1 protease inhibitor/cobicistat combination, consider an alternative HCV or antiretroviral therapy, as the safety of increased tenofovir concentrations in this setting has not been established. If coadministration is necessary, monitor for adverse reactions associated with TDF.

8 USE IN SPECIFIC POPULATIONS

8.1 Pregnancy

Pregnancy Exposure Registry

There is a pregnancy exposure registry that monitors pregnancy outcomes in women exposed to TRUVADA during pregnancy. Healthcare providers are encouraged to register patients by calling the Antiretroviral Pregnancy Registry (APR) at 1-800-258-4263.

Risk Summary

Data on the use of TRUVADA during pregnancy from observational studies have shown no increased risk of major birth defects. Available data from the APR show no significant difference in the overall risk of major birth defects with first trimester exposure for emtricitabine (FTC) (2.3%) or tenofovir disoproxil fumarate (TDF) (2.1%) compared with the background rate for major birth defects of 2.7% in a U.S. reference population of the Metropolitan Atlanta Congenital Defects Program (MACDP) (see Data). The rate of miscarriage for individual drugs is not reported in the APR. In the U.S. general population, the estimated background risk of miscarriage in clinically recognized pregnancies is 15–20%.

In animal reproduction studies, no adverse developmental effects were observed when the components of TRUVADA were administered separately at doses/exposures ≥60 (FTC), ≥14 (TDF) and 2.7 (tenofovir) times those of the recommended daily dose of TRUVADA (see Data).

Clinical Considerations

Disease-associated maternal and/or embryo/fetal risk

HIV-1 PrEP: Published studies indicate an increased risk of HIV-1 infection during pregnancy and an increased risk of mother to child transmission during acute HIV-1 infection. In women at risk of acquiring HIV-1, consideration should be given to methods to prevent acquisition of HIV, including continuing or initiating TRUVADA for HIV-1 PrEP, during pregnancy.

Data

Human Data

TRUVADA for HIV-1 PrEP: In an observational study based on prospective reports to the APR, 78 HIV-seronegative women exposed to TRUVADA during pregnancy delivered live-born infants with no major malformations. All but one were first trimester exposures, and the median duration of exposure was 10.5 weeks. There were no new safety findings in the women receiving TRUVADA for HIV-1 PrEP compared with HIV-1 infected women treated with other antiretroviral medications.

Emtricitabine: Based on prospective reports to the APR of exposures to FTC-containing regimens during pregnancy resulting in live births (including over 3,300 exposed in the first trimester and over 1,300 exposed in the second/third trimester), the prevalence of major birth defects in live births was 2.6% (95% CI: 2.1% to 3.2%) and 2.3% (95% CI: 1.6% to 3.3%) following first and second/third trimester exposure, respectively, to FTC-containing regimens.

Tenofovir Disoproxil Fumarate: Based on prospective reports to the APR of exposures to TDF-containing regimens during pregnancy resulting in live births (including over 4,000 exposed in the first trimester and over 1,700 exposed in the second/third trimester), the prevalence of major birth defects in live births was 2.4% (95% CI: 2.0% to 2.9%) and 2.4% (95% CI: 1.7% to 3.2%) following first and second/third trimester exposure, respectively, to TDF-containing regimens.

Methodologic limitations of the APR include the use of MACDP as the external comparator group. The MACDP population is not disease-specific, evaluates women and infants from a limited geographic area, and does not include outcomes for births that occurred at <20 weeks gestation.

Additionally, published observational studies on emtricitabine and tenofovir exposure in pregnancy have not shown an increased risk for major malformations.

Animal Data

Emtricitabine: FTC was administered orally to pregnant mice (at 0, 250, 500, or 1,000 mg/kg/day), and rabbits (at 0, 100, 300, or 1,000 mg/kg/day) through organogenesis (on gestation days 6 through 15, and 7 through 19, respectively). No significant toxicological effects were observed in embryo-fetal toxicity studies performed with FTC in mice at exposures (AUC) approximately 60 times higher and in rabbits at approximately 120 times higher than human exposures at the recommended daily dose. In a pre/postnatal development study in mice, FTC was administered orally at doses up to 1,000 mg/kg/day; no significant adverse effects directly related to drug were observed in the offspring exposed daily from before birth (in utero) through sexual maturity at daily exposures (AUC) of approximately 60 times higher than human exposures at the recommended daily dose.

Tenofovir Disoproxil Fumarate: TDF was administered orally to pregnant rats (at 0, 50, 150, or 450 mg/kg/day) and rabbits (at 0, 30, 100, or 300 mg/kg/day) through organogenesis (on gestation days 7 through 17, and 6 through 18, respectively). No significant toxicological effects were observed in embryo-fetal toxicity studies performed with TDF in rats at doses up to 14 times the human dose based on body surface area comparisons and in rabbits at doses up to 19 times the human dose based on body surface area comparisons. In a pre/postnatal development study in rats, TDF was administered orally through lactation at doses up to 600 mg/kg/day; no adverse effects were observed in the offspring at tenofovir exposures of approximately 2.7 times higher than human exposures at the recommended daily dose of TRUVADA.

8.2 Lactation

Risk Summary

Based on published data, FTC and tenofovir have been shown to be present in human breast milk (see Data). It is not known if the components of TRUVADA affect milk production or have effects on the breastfed child.

Treatment of HIV-1 Infection:

The Centers for Disease Control and Prevention recommend that HIV-1 infected mothers not breastfeed their infants to avoid risking postnatal transmission of HIV-1.

Because of the potential for: (1) HIV transmission (in HIV-negative infants); (2) developing viral resistance (in HIV-positive infants); and (3) adverse reactions in a breastfed infant similar to those seen in adults, instruct mothers not to breastfeed if they are taking TRUVADA for the treatment of HIV-1.

HIV-1 PrEP:

In HIV-uninfected women, the developmental and health benefits of breastfeeding and the mother's clinical need for TRUVADA for HIV-1 PrEP should be considered along with any potential adverse effects on the breastfed child from TRUVADA and the risk of HIV-1 acquisition due to nonadherence and subsequent mother to child transmission.

Women should not breastfeed if acute HIV-1 infection is suspected because of the risk of HIV-1 transmission to the infant.

Data

HIV-1 PrEP: In a study of 50 breastfeeding women who received TRUVADA for HIV-1 PrEP between 1 and 24 weeks postpartum (median 13 weeks), after 7 days of treatment, tenofovir was undetectable but FTC was detectable in the plasma of most infants. In these infants, the average FTC plasma concentration was less than 1% of the FTC Cmax observed in HIV-infected infants (up to 3 months of age) receiving the therapeutic dose of FTC (3 mg/kg/day). There were no serious adverse events. Two infants (4%) had an adverse event of mild diarrhea which resolved.

8.4 Pediatric Use

Treatment of HIV-1 Infection

No pediatric clinical trial was conducted to evaluate the safety and efficacy of TRUVADA in patients with HIV-1 infection. Data from previously conducted trials with the individual drug products, FTC and TDF, were relied upon to support dosage recommendations for TRUVADA. For additional information, consult the prescribing information for EMTRIVA and VIREAD.

TRUVADA should only be administered to HIV-1 infected pediatric patients with body weight greater than or equal to 17 kg and who are able to swallow a tablet. Because it is a fixed-dose combination tablet, TRUVADA cannot be adjusted for patients of lower weight [see Warnings and Precautions (5.5), Adverse Reactions (6.1) and Clinical Pharmacology (12.3)]. TRUVADA is not approved for use in pediatric patients weighing less than 17 kg.

HIV-1 PrEP

The safety and effectiveness of TRUVADA for HIV-1 PrEP in at-risk adolescents weighing at least 35 kg is supported by data from adequate and well-controlled studies of TRUVADA for HIV-1 PrEP in adults with additional data from safety and pharmacokinetic studies in previously conducted trials with the individual drug products, FTC and TDF, in HIV-1 infected adults and pediatric subjects [see Dosage and Administration (2.5), Adverse Reactions (6.1), Clinical Pharmacology (12.3 and 12.4), and Clinical Studies (14.3 and 14.4)].

Safety, adherence, and resistance were evaluated in a single-arm, open-label clinical trial (ATN113) in which 67 HIV-1 uninfected at-risk adolescent men who have sex with men received TRUVADA once daily for HIV-1 PrEP. The mean age of subjects was 17 years (range 15 to 18 years); 46% were Hispanic, 52% Black, and 37% White. The safety profile of TRUVADA in ATN113 was similar to that observed in the adult HIV-1 PrEP trials [see Adverse Reactions (6.1)].

In the ATN113 trial, HIV-1 seroconversion occurred in 3 subjects. Tenofovir diphosphate levels in dried blood spot assays indicate that these subjects had poor adherence. No tenofovir- or FTC-associated HIV-1 resistance substitutions were detected in virus isolated from the 3 subjects who seroconverted [see Microbiology (12.4)].

Adherence to study drug, as demonstrated by tenofovir diphosphate levels in dried blood spot assays, declined markedly after Week 12 once subjects switched from monthly to quarterly visits, suggesting that adolescents may benefit from more frequent visits and counseling [see Warnings and Precautions (5.2)].

Safety and effectiveness of Truvada for HIV-1 PrEP in pediatric patients weighing less than 35 kg have not been established.

8.5 Geriatric Use

Clinical trials of FTC, TDF, or TRUVADA did not include sufficient numbers of subjects aged 65 and over to determine whether they respond differently from younger subjects.

8.6 Renal Impairment

Treatment of HIV-1 Infection

The dosing interval for TRUVADA should be modified in HIV-infected adult individuals with estimated creatinine clearance of 30–49 mL/min. TRUVADA is not recommended in individuals with estimated creatinine clearance below 30 mL/min and in individuals with end-stage renal disease requiring dialysis [see Dosage and Administration (2.6)].

HIV-1 PrEP

TRUVADA for HIV-1 PrEP is not recommended in HIV-1 uninfected individuals with estimated creatinine clearance below 60 mL/min. If a decrease in estimated creatinine clearance is observed in uninfected individuals while using TRUVADA for HIV-1 PrEP, evaluate potential causes and re-assess potential risks and benefits of continued use [see Dosage and Administration (2.6)].

10 OVERDOSAGE

If overdose occurs, the patient must be monitored for evidence of toxicity, and standard supportive treatment applied as necessary.

Emtricitabine: Hemodialysis treatment removes approximately 30% of the FTC dose over a 3-hour dialysis period starting within 1.5 hours of FTC dosing (blood flow rate of 400 mL/min and a dialysate flow rate of 600 mL/min). It is not known whether FTC can be removed by peritoneal dialysis.

Tenofovir Disoproxil Fumarate: Tenofovir is efficiently removed by hemodialysis with an extraction coefficient of approximately 54%. Following a single 300 mg dose of TDF, a four-hour hemodialysis session removed approximately 10% of the administered tenofovir dose.

11 DESCRIPTION

TRUVADA tablets are fixed-dose combination tablets containing emtricitabine (FTC) and tenofovir disoproxil fumarate (TDF). FTC is a synthetic nucleoside analog of cytidine. TDF is converted in vivo to tenofovir, an acyclic nucleoside phosphonate (nucleotide) analog of adenosine 5′-monophosphate. Both FTC and tenofovir exhibit inhibitory activity against HIV-1 reverse transcriptase.

Emtricitabine: The chemical name of FTC is 5-fluoro-1-(2R,5S)-[2-(hydroxymethyl)-1,3-oxathiolan-5-yl]cytosine. FTC is the (-) enantiomer of a thio analog of cytidine, which differs from other cytidine analogs in that it has a fluorine in the 5-position.

It has a molecular formula of C8H10FN3O3S and a molecular weight of 247.24. It has the following structural formula:

FTC is a white to off-white crystalline powder with a solubility of approximately 112 mg/mL in water at 25 °C. The partition coefficient (log p) for emtricitabine is −0.43 and the pKa is 2.65.

Tenofovir Disoproxil Fumarate: TDF is a fumaric acid salt of the bis-isopropoxycarbonyloxymethyl ester derivative of tenofovir. The chemical name of tenofovir DF is 9-[(R)-2 [[bis[[(isopropoxycarbonyl)oxy]- methoxy]phosphinyl]methoxy]propyl]adenine fumarate (1:1). It has a molecular formula of C19H30N5O10P ∙ C4H4O4 and a molecular weight of 635.52. It has the following structural formula:

Tenofovir disoproxil fumarate is a white to off-white crystalline powder with a solubility of 13.4 mg/mL in water at 25 °C. The partition coefficient (log p) for tenofovir disoproxil is 1.25 and the pKa is 3.75. All dosages are expressed in terms of TDF except where otherwise noted.

TRUVADA tablets are for oral administration, and are available in the following strengths:

- Film-coated tablet containing 200 mg of FTC and 300 mg of TDF (which is equivalent to 245 mg of tenofovir disoproxil) as active ingredients
- Film-coated tablet containing 167 mg of FTC and 250 mg of TDF (which is equivalent to 204 mg of tenofovir disoproxil) as active ingredients
- Film-coated tablet containing 133 mg of FTC and 200 mg of TDF (which is equivalent to 163 mg of tenofovir disoproxil) as active ingredients
- Film-coated tablet containing 100 mg of FTC and 150 mg of TDF (which is equivalent to 123 mg of tenofovir disoproxil) as active ingredients

All strengths of TRUVADA tablets also include the following inactive ingredients: croscarmellose sodium, lactose monohydrate, magnesium stearate, microcrystalline cellulose, and pregelatinized starch (gluten free). The 200 mg/300 mg strength tablets are coated with Opadry II Blue Y-30-10701, which contains FD&C Blue #2 aluminum lake, hypromellose 2910, lactose monohydrate, titanium dioxide, and triacetin. The 167 mg/250 mg, 133 mg/200 mg, and 100 mg/150 mg strength tablets are coated with Opadry II Blue, which contains FD&C Blue #2 aluminum lake, hypromellose 2910, lactose monohydrate, titanium dioxide, and triacetin.

12 CLINICAL PHARMACOLOGY

12.1 Mechanism of Action

TRUVADA is a fixed-dose combination of antiviral drugs FTC and TDF [see Microbiology (12.4)].

12.3 Pharmacokinetics

TRUVADA: One TRUVADA tablet was comparable to one FTC capsule (200 mg) plus one TDF tablet (300 mg) following single-dose administration to fasting healthy subjects (N=39).

Emtricitabine: The pharmacokinetic properties of FTC are summarized in Table 8. Following oral administration of FTC, FTC is rapidly absorbed with peak plasma concentrations occurring at 1–2 hours postdose. Less than 4% of FTC binds to human plasma proteins in vitro, and the binding is independent of concentration over the range of 0.02–200 μg/mL. Following administration of radiolabelled FTC, approximately 86% is recovered in the urine and 13% is recovered as metabolites. The metabolites of FTC include 3′-sulfoxide diastereomers and their glucuronic acid conjugate. Emtricitabine is eliminated by a combination of glomerular filtration and active tubular secretion. Following a single oral dose of FTC, the plasma FTC half-life is approximately 10 hours.

Tenofovir Disoproxil Fumarate: The pharmacokinetic properties of TDF are summarized in Table 8. Following oral administration of TDF, maximum tenofovir serum concentrations are achieved in 1.0 ± 0.4 hour. Less than 0.7% of tenofovir binds to human plasma proteins in vitro, and the binding is independent of concentration over the range of 0.01–25 µg/mL. Approximately 70–80% of the intravenous dose of tenofovir is recovered as unchanged drug in the urine. Tenofovir is eliminated by a combination of glomerular filtration and active tubular secretion. Following a single oral dose of TDF, the terminal elimination half-life of tenofovir is approximately 17 hours.

Table 8 Single Dose Pharmacokinetic Parameters for FTC and Tenofovir in Adults [NC=Not calculated]
 | FTC | Tenofovir
Fasted Oral Bioavailability [Median (range)] (%) | 92 (83.1–106.4) | 25 (NC–45.0)
Plasma Terminal Elimination Half-Life (hr) | 10 (7.4–18.0) | 17 (12.0–25.7)
Cmax [Mean (± SD)] (μg/mL) | 1.8±0.72 [Data presented as steady state values] | 0.30±0.09
AUC (μg∙hr/mL) | 10.0±3.12 | 2.29±0.69
CL/F (mL/min) | 302±94 | 1043±115
CLrenal (mL/min) | 213±89 | 243±33

Effects of Food on Oral Absorption

TRUVADA may be administered with or without food. Administration of TRUVADA following a high fat meal (784 kcal; 49 grams of fat) or a light meal (373 kcal; 8 grams of fat) delayed the time of tenofovir Cmax by approximately 0.75 hour. The mean increases in tenofovir AUC and Cmax were approximately 35% and 15%, respectively, when administered with a high fat or light meal, compared to administration in the fasted state. In previous safety and efficacy trials, TDF (tenofovir) was taken under fed conditions. FTC systemic exposures (AUC and Cmax) were unaffected when TRUVADA was administered with either a high fat or a light meal.

Specific Populations

Race

Emtricitabine: No pharmacokinetic differences due to race have been identified following the administration of FTC.

Tenofovir Disoproxil Fumarate: There were insufficient numbers from racial and ethnic groups other than Caucasian to adequately determine potential pharmacokinetic differences among these populations following the administration of TDF.

Gender

Emtricitabine and Tenofovir Disoproxil Fumarate: FTC and tenofovir pharmacokinetics are similar in male and female subjects.

Pediatric Patients

Treatment of HIV-1 Infection: The pharmacokinetic data for tenofovir and FTC following administration of TRUVADA in pediatric subjects weighing 17 kg and above are not available. The dosage recommendations of TRUVADA in this population are based on the dosage recommendations of FTC and TDF in this population. Refer to the EMTRIVA and VIREAD prescribing information for pharmacokinetic information on the individual products in pediatric patients.

HIV-1 PrEP: The pharmacokinetic data for tenofovir and FTC following administration of TRUVADA in HIV-1 uninfected adolescents weighing 35 kg and above are not available. The dosage recommendations of TRUVADA for HIV-1 PrEP in this population are based on safety and adherence data from the ATN113 trial [see Use in Specific Populations (8.4)] and known pharmacokinetic information in HIV-infected adolescents taking TDF and FTC for treatment.

Geriatric Patients

Pharmacokinetics of FTC and tenofovir have not been fully evaluated in the elderly (65 years of age and older).

Patients with Renal Impairment

The pharmacokinetics of FTC and tenofovir are altered in subjects with renal impairment [see Warnings and Precautions (5.3)]. In adult subjects with creatinine clearance below 50 mL/min, Cmax and AUC0–∞ of FTC and tenofovir were increased. No data are available to make dosage recommendations in pediatric patients with renal impairment.

Patients with Hepatic Impairment

The pharmacokinetics of tenofovir following a 300 mg dose of TDF have been studied in non-HIV infected subjects with moderate to severe hepatic impairment. There were no substantial alterations in tenofovir pharmacokinetics in subjects with hepatic impairment compared with unimpaired subjects. The pharmacokinetics of TRUVADA or FTC have not been studied in subjects with hepatic impairment; however, FTC is not significantly metabolized by liver enzymes, so the impact of liver impairment should be limited.

Assessment of Drug Interactions

The steady state pharmacokinetics of FTC and tenofovir were unaffected when FTC and TDF were administered together versus each agent dosed alone.

In vitro studies and clinical pharmacokinetic drug-drug interaction trials have shown that the potential for CYP mediated interactions involving FTC and tenofovir with other medicinal products is low.

TDF is a substrate of P-glycoprotein (P-gp) and breast cancer resistance protein (BCRP) transporters. When TDF is coadministered with an inhibitor of these transporters, an increase in absorption may be observed.

No clinically significant drug interactions have been observed between FTC and famciclovir, indinavir, stavudine, TDF, and zidovudine (Tables 9 and 10). Similarly, no clinically significant drug interactions have been observed between TDF and efavirenz, methadone, nelfinavir, oral contraceptives, ribavirin, or sofosbuvir in trials conducted in healthy volunteers (Tables 11 and 12).

Table 9 Drug Interactions: Changes in Pharmacokinetic Parameters for FTC in the Presence of the Coadministered Drug [All interaction trials conducted in healthy volunteers]
Coadministered Drug | Dose of Coadministered Drug (mg) | FTC Dose (mg) | N | % Change of FTC Pharmacokinetic Parameters [↑ = Increase; ⇔ = No Effect; NA = Not Applicable] (90% CI)
Coadministered Drug | Dose of Coadministered Drug (mg) | FTC Dose (mg) | N | Cmax | AUC | Cmin
TDF | 300 once daily × 7 days | 200 once daily × 7 days | 17 | ⇔ | ⇔ | ↑ 20 (↑ 12 to ↑ 29)
Zidovudine | 300 twice daily × 7 days | 200 once daily × 7 days | 27 | ⇔ | ⇔ | ⇔
Indinavir | 800 × 1 | 200 × 1 | 12 | ⇔ | ⇔ | NA
Famciclovir | 500 × 1 | 200 × 1 | 12 | ⇔ | ⇔ | NA
Stavudine | 40 × 1 | 200 × 1 | 6 | ⇔ | ⇔ | NA

Table 10 Drug Interactions: Changes in Pharmacokinetic Parameters for Coadministered Drug in the Presence of FTC [All interaction trials conducted in healthy volunteers]
Coadministered Drug | Dose of Coadministered Drug (mg) | FTC Dose (mg) | N | % Change of Coadministered Drug Pharmacokinetic Parameters [↑ = Increase; ⇔ = No Effect; NA = Not Applicable] (90% CI)
Coadministered Drug | Dose of Coadministered Drug (mg) | FTC Dose (mg) | N | Cmax | AUC | Cmin
TDF | 300 once daily × 7 days | 200 once daily × 7 days | 17 | ⇔ | ⇔ | ⇔
Zidovudine | 300 twice daily × 7 days | 200 once daily × 7 days | 27 | ↑ 17 (↑ 0 to ↑ 38) | ↑ 13 (↑ 5 to ↑ 20) | ⇔
Indinavir | 800 × 1 | 200 × 1 | 12 | ⇔ | ⇔ | NA
Famciclovir | 500 × 1 | 200 × 1 | 12 | ⇔ | ⇔ | NA
Stavudine | 40 × 1 | 200 × 1 | 6 | ⇔ | ⇔ | NA

Table 11 Drug Interactions: Changes in Pharmacokinetic Parameters for Tenofovir [Subjects received VIREAD 300 mg once daily.] in the Presence of the Coadministered Drug
Coadministered Drug | Dose of Coadministered Drug (mg) | N | % Change of Tenofovir Pharmacokinetic Parameters [Increase = ↑; Decrease = ↓; No Effect = ⇔] (90% CI)
Coadministered Drug | Dose of Coadministered Drug (mg) | N | Cmax | AUC | Cmin
Atazanavir [Reyataz Prescribing Information.] | 400 once daily × 14 days | 33 | ↑ 14 (↑ 8 to ↑ 20) | ↑ 24 (↑ 21 to ↑ 28) | ↑ 22 (↑ 15 to ↑ 30)
Atazanavir/ Ritonavir | 300/100 once daily | 12 | ↑ 34 (↑ 20 to ↑ 51) | ↑ 37 (↑ 30 to ↑ 45) | ↑ 29 (↑ 21 to ↑ 36)
Darunavir/ Ritonavir [Prezista Prescribing Information.] | 300/100 twice daily | 12 | ↑ 24 (↑ 8 to ↑ 42) | ↑ 22 (↑ 10 to ↑ 35) | ↑ 37 (↑ 19 to ↑ 57)
Indinavir | 800 three times daily × 7 days | 13 | ↑ 14 (↓ 3 to ↑ 33) | ⇔ | ⇔
Ledipasvir/ Sofosbuvir [Data generated from simultaneous dosing with HARVONI (ledipasvir/sofosbuvir). Staggered administration (12 hours apart) provided similar results.] , [Comparison based on exposures when administered as atazanavir/ritonavir + FTC/TDF.] | 90/400 once daily × 10 days | 24 | ↑ 47 (↑ 37 to ↑ 58) | ↑ 35 (↑ 29 to ↑42) | ↑ 47 (↑ 38 to ↑ 57)
Ledipasvir/ Sofosbuvir, [Comparison based on exposures when administered as darunavir/ritonavir + FTC/TDF.] | 90/400 once daily × 10 days | 23 | ↑ 64 (↑ 54 to ↑ 74) | ↑ 50 (↑ 42 to ↑ 59) | ↑ 59 (↑ 49 to ↑ 70)
Ledipasvir/ Sofosbuvir [Study conducted with ATRIPLA (efavirenz/FTC/TDF) coadministered with HARVONI.] | 90/400 once daily × 14 days | 15 | ↑ 79 (↑ 56 to ↑ 104) | ↑ 98 (↑ 77 to ↑ 123) | ↑ 163 (↑ 132 to ↑ 197)
Ledipasvir/ Sofosbuvir [Study conducted with COMPLERA (FTC/rilpivirine/TDF) coadministered with HARVONI.] | 90/400 once daily × 10 days | 14 | ↑ 32 (↑ 25 to ↑ 39) | ↑ 40 (↑ 31 to ↑ 50) | ↑ 91 (↑ 74 to ↑ 110)
Ledipasvir/ Sofosbuvir [Study conducted with TRUVADA (FTC/TDF) + dolutegravir coadministered with HARVONI.] | 90/400 once daily × 10 days | 29 | ↑ 61 (↑ 51 to ↑ 72) | ↑ 65 (↑ 59 to ↑ 71) | ↑ 115 (↑ 105 to ↑ 126)
Lopinavir/ Ritonavir | 400/100 twice daily × 14 days | 24 | ⇔ | ↑ 32 (↑ 25 to ↑ 38) | ↑ 51 (↑ 37 to ↑ 66)
Saquinavir/ Ritonavir | 1000/100 twice daily × 14 days | 35 | ⇔ | ⇔ | ↑ 23 (↑ 16 to ↑ 30)
Sofosbuvir [Study conducted with ATRIPLA coadministered with SOVALDI® (sofosbuvir).] | 400 single dose | 16 | ↑ 25 (↑ 8 to ↑ 45) | ⇔ | ⇔
Sofosbuvir/ Velpatasvir [Study conducted with COMPLERA coadministered with EPCLUSA; coadministration with EPCLUSA also results in comparable increases in tenofovir exposures when TDF is administered as ATRIPLA, STRIBILD, TRUVADA + atazanavir/ritonavir, or TRUVADA + darunavir/ritonavir.] | 400/100 once daily | 24 | ↑ 44 (↑ 33 to ↑ 55) | ↑ 40 (↑ 34 to ↑ 46) | ↑ 84 (↑ 76 to ↑ 92)
Sofosbuvir/ Velpatasvir [Administered as raltegravir + FTC/TDF.] | 400/100 once daily | 30 | ↑ 46 (↑ 39 to ↑ 54) | ↑ 40 (↑ 34 to ↑ 45) | ↑ 70 (↑ 61 to ↑ 79)
Sofosbuvir/ Velpatasvir/Voxilaprevir [Comparison based on exposures when administered as darunavir + ritonavir + FTC/TDF.] | 400/100/100 + Voxilaprevir [Study conducted with additional voxilaprevir 100 mg to achieve voxilaprevir exposures expected in HCV-infected patients] 100 once daily | 29 | ↑ 48 (↑ 36 to ↑ 61) | ↑ 39 (↑ 32 to ↑ 46) | ↑ 47 (↑ 38 to ↑ 56)
Tacrolimus | 0.05 mg/kg twice daily × 7 days | 21 | ↑ 13 (↑ 1 to ↑ 27) | ⇔ | ⇔
Tipranavir/ Ritonavir [Aptivus Prescribing Information.] | 500/100 twice daily | 22 | ↓ 23 (↓ 32 to ↓ 13) | ↓ 2 (↓ 9 to ↑ 5) | ↑ 7 (↓ 2 to ↑ 17)
Tipranavir/ Ritonavir [Aptivus Prescribing Information.] | 750/200 twice daily (23 doses) | 20 | ↓ 38 (↓ 46 to ↓ 29) | ↑ 2 (↓ 6 to ↑ 10) | ↑ 14 (↑ 1 to ↑ 27)

No effect on the pharmacokinetic parameters of the following coadministered drugs was observed with TRUVADA: abacavir, didanosine (buffered tablets), FTC, entecavir, and lamivudine.

Table 12 Drug Interactions: Changes in Pharmacokinetic Parameters for Coadministered Drug in the Presence of Tenofovir
Coadministered Drug | Dose of Coadministered Drug (mg) | N | % Change of Coadministered Drug Pharmacokinetic Parameters [Increase = ↑; Decrease = ↓; No Effect = ⇔; NA = Not Applicable] (90% CI)
Coadministered Drug | Dose of Coadministered Drug (mg) | N | Cmax | AUC | Cmin
Abacavir | 300 once | 8 | ↑ 12 (↓ 1 to ↑ 26) | ⇔ | NA
Atazanavir [Reyataz Prescribing Information.] | 400 once daily × 14 days | 34 | ↓ 21 (↓ 27 to ↓ 14) | ↓ 25 (↓ 30 to ↓ 19) | ↓ 40 (↓ 48 to ↓ 32)
Atazanavir | Atazanavir/Ritonavir 300/100 once daily × 42 days | 10 | ↓ 28 (↓ 50 to ↑ 5) | ↓ 25 [In HIV-infected subjects, addition of TDF to atazanavir 300 mg plus ritonavir 100 mg resulted in AUC and Cmin values of atazanavir that were 2.3- and 4-fold higher than the respective values observed for atazanavir 400 mg when given alone.] (↓ 42 to ↓ 3) | ↓ 23 (↓ 46 to ↑ 10)
Darunavir [Prezista Prescribing Information.] | Darunavir/Ritonavir 300/100 once daily | 12 | ↑ 16 (↓ 6 to ↑ 42) | ↑ 21 (↓ 5 to ↑ 54) | ↑ 24 (↓ 10 to ↑ 69)
Didanosine [Videx EC Prescribing Information. Subjects received didanosine enteric-coated capsules. When didanosine 250 mg enteric-coated capsules were administered with TDF, systemic exposures of didanosine were similar to those seen with the 400 mg enteric-coated capsules alone under fasted conditions.] | 250 once, simultaneously with TDF and a light meal [373 kcal, 8.2 g fat] | 33 | ↓ 20 [Compared with didanosine (enteric-coated) 400 mg administered alone under fasting conditions.] (↓ 32 to ↓ 7) | ⇔ | NA
Emtricitabine | 200 once daily × 7 days | 17 | ⇔ | ⇔ | ↑ 20 (↑ 12 to ↑ 29)
Indinavir | 800 three times daily × 7 days | 12 | ↓ 11 (↓ 30 to ↑ 12) | ⇔ | ⇔
Entecavir | 1 once daily × 10 days | 28 | ⇔ | ↑ 13 (↑ 11 to ↑ 15) | ⇔
Lamivudine | 150 twice daily × 7 days | 15 | ↓ 24 (↓ 34 to ↓ 12) | ⇔ | ⇔
Lopinavir | Lopinavir/Ritonavir 400/100 twice daily × 14 days | 24 | ⇔ | ⇔ | ⇔
Ritonavir | Lopinavir/Ritonavir 400/100 twice daily × 14 days | 24 | ⇔ | ⇔ | ⇔
Saquinavir | Saquinavir/Ritonavir 1000/100 twice daily × 14 days | 32 | ↑ 22 (↑ 6 to ↑41) | ↑ 29 [Increases in AUC and Cmin are not expected to be clinically relevant; hence, no dose adjustments are required when TDF and ritonavir-boosted saquinavir are coadministered.] (↑ 12 to ↑ 48) | ↑ 47 (↑ 23 to ↑ 76)
Ritonavir | Saquinavir/Ritonavir 1000/100 twice daily × 14 days | 32 | ⇔ | ⇔ | ↑ 23 (↑ 3 to ↑ 46)
Tacrolimus | 0.05 mg/kg twice daily × 7 days | 21 | ⇔ | ⇔ | ⇔
Tipranavir [Aptivus Prescribing Information.] | Tipranavir/Ritonavir 500/100 twice daily | 22 | ↓ 17 (↓ 26 to ↓ 6) | ↓ 18 (↓ 25 to ↓ 9) | ↓ 21 (↓ 30 to ↓ 10)
Tipranavir [Aptivus Prescribing Information.] | Tipranavir/Ritonavir 750/200 twice daily (23 doses) | 20 | ↓ 11 (↓ 16 to ↓ 4) | ↓ 9 (↓ 15 to ↓ 3) | ↓ 12 (↓ 22 to 0)

12.4 Microbiology

Mechanism of Action

Emtricitabine: FTC, a synthetic nucleoside analog of cytidine, is phosphorylated by cellular enzymes to form emtricitabine 5'-triphosphate (FTC-TP), which inhibits the activity of the HIV-1 reverse transcriptase (RT) by competing with the natural substrate deoxycytidine 5'-triphosphate and by being incorporated into nascent viral DNA which results in chain termination. FTC-TP is a weak inhibitor of mammalian DNA polymerases α, β, ε and mitochondrial DNA polymerase γ.

Tenofovir Disoproxil Fumarate: TDF is an acyclic nucleoside phosphonate diester analog of adenosine monophosphate. TDF requires initial diester hydrolysis for conversion to tenofovir and subsequent phosphorylations by cellular enzymes to form tenofovir diphosphate (TFV-DP), which inhibits the activity of HIV-1 RT by competing with the natural substrate deoxyadenosine 5′-triphosphate and, after incorporation into DNA, by DNA chain termination. TFV-DP is a weak inhibitor of mammalian DNA polymerases α, β, and mitochondrial DNA polymerase γ.

Antiviral Activity

Emtricitabine and Tenofovir Disoproxil Fumarate: No antagonism was observed in combination studies evaluating the cell culture antiviral activity of FTC and tenofovir together.

Emtricitabine: The antiviral activity of FTC against laboratory and clinical isolates of HIV-1 was assessed in lymphoblastoid cell lines, the MAGI-CCR5 cell line, and peripheral blood mononuclear cells. The 50% effective concentration (EC50) values for FTC were in the range of 0.0013–0.64 µM (0.0003–0.158 µg/mL). In drug combination studies of FTC with nucleoside RT inhibitors (abacavir, lamivudine, stavudine, zidovudine), non-nucleoside RT inhibitors (delavirdine, efavirenz, nevirapine), and protease inhibitors (amprenavir, nelfinavir, ritonavir, saquinavir), no antagonism was observed. Emtricitabine displayed antiviral activity in cell culture against HIV-1 clades A, B, C, D, E, F, and G (EC50 values ranged from 0.007–0.075 µM) and showed strain-specific activity against HIV-2 (EC50 values ranged from 0.007–1.5 µM).

Tenofovir Disoproxil Fumarate: The antiviral activity of tenofovir against laboratory and clinical isolates of HIV-1 was assessed in lymphoblastoid cell lines, primary monocyte/macrophage cells, and peripheral blood lymphocytes. The EC50 values for tenofovir were in the range of 0.04–8.5 µM. In drug combination studies of tenofovir with nucleoside RT inhibitors (abacavir, didanosine, lamivudine, stavudine, zidovudine), non-nucleoside RT inhibitors (delavirdine, efavirenz, nevirapine), and protease inhibitors (amprenavir, indinavir, nelfinavir, ritonavir, saquinavir), no antagonism was observed. Tenofovir displayed antiviral activity in cell culture against HIV-1 clades A, B, C, D, E, F, G, and O (EC50 values ranged from 0.5–2.2 µM) and showed strain-specific activity against HIV-2 (EC50 values ranged from 1.6 µM to 5.5 µM).

Prophylactic Activity in a Nonhuman Primate Model of HIV-1 Transmission

Emtricitabine and Tenofovir Disoproxil Fumarate: The prophylactic activity of the combination of daily oral FTC and TDF was evaluated in a controlled study of macaques inoculated once weekly for 14 weeks with SIV/HIV-1 chimeric virus (SHIV) applied to the rectal surface. Of the 18 control animals, 17 became infected after a median of 2 weeks. In contrast, 4 of the 6 animals treated daily with oral FTC and TDF remained uninfected and the two infections that did occur were significantly delayed until 9 and 12 weeks and exhibited reduced viremia. An M184I-expressing FTC-resistant variant emerged in 1 of the 2 macaques after 3 weeks of continued drug exposure.

Resistance

Emtricitabine and Tenofovir Disoproxil Fumarate: HIV-1 isolates with reduced susceptibility to the combination of FTC and tenofovir have been selected in cell culture. Genotypic analysis of these isolates identified the M184V/I and/or K65R amino acid substitutions in the viral RT. In addition, a K70E substitution in the HIV-1 RT has been selected by tenofovir and results in reduced susceptibility to tenofovir.

In Study 934, a clinical trial of treatment-naïve subjects [see Clinical Studies (14.2)], resistance analysis was performed on HIV-1 isolates from all confirmed virologic failure subjects with greater than 400 copies/mL of HIV-1 RNA at Week 144 or early discontinuation. Development of efavirenz resistance-associated substitutions occurred most frequently and was similar between the treatment arms. The M184V amino acid substitution, associated with resistance to FTC and lamivudine, was observed in 2/19 analyzed subject isolates in the FTC+TDF group and in 10/29 analyzed subject isolates in the zidovudine/lamivudine group. Through 144 weeks of Study 934, no subjects have developed a detectable K65R or K70E substitution in their HIV-1 as analyzed through standard genotypic analysis.

Emtricitabine: FTC-resistant isolates of HIV-1 have been selected in cell culture and in vivo. Genotypic analysis of these isolates showed that the reduced susceptibility to FTC was associated with a substitution in the HIV-1 RT gene at codon 184 which resulted in an amino acid substitution of methionine by valine or isoleucine (M184V/I).

Tenofovir Disoproxil Fumarate: HIV-1 isolates with reduced susceptibility to tenofovir have been selected in cell culture. These viruses expressed a K65R substitution in RT and showed a 2- to 4-fold reduction in susceptibility to tenofovir.

In treatment-naïve subjects, isolates from 8/47 (17%) analyzed subjects developed the K65R substitution in the TDF arm through 144 weeks; 7 occurred in the first 48 weeks of treatment and 1 at Week 96. In treatment-experienced subjects, 14/304 (5%) isolates from subjects failing TDF through Week 96 showed greater than 1.4-fold (median 2.7) reduced susceptibility to tenofovir. Genotypic analysis of the resistant isolates showed a K65R amino acid substitution in the HIV-1 RT.

iPrEx Trial: In the iPrEx trial, a clinical trial of HIV-1 seronegative adult subjects [see Clinical Studies (14.3)], no amino acid substitutions associated with resistance to FTC or TDF were detected at the time of seroconversion among 48 subjects in the TRUVADA group and 83 subjects in the placebo group who became infected with HIV-1 during the trial. Ten subjects were observed to be HIV-1 infected at time of enrollment. The M184V/I substitutions associated with resistance to FTC were observed in 3 of the 10 subjects (2 of 2 in the TRUVADA group and 1 of 8 in the placebo group). One of the two subjects in the TRUVADA group harbored wild type virus at enrollment and developed the M184V substitution 4 weeks after enrollment. The other subject had indeterminate resistance at enrollment but was found to have the M184I substitution 4 weeks after enrollment.

Partners PrEP Trial: In the Partners PrEP trial, a clinical trial of HIV-1 seronegative adult subjects [see Clinical Studies (14.4)], no variants expressing amino acid substitutions associated with resistance to FTC or TDF were detected at the time of seroconversion among 12 subjects in the TRUVADA group, 15 subjects in the TDF group, and 51 subjects in the placebo group. Fourteen subjects were observed to be HIV-1 infected at the time of enrollment (3 in the TRUVADA group, 5 in the TDF group, and 6 in the placebo group). One of the three subjects in the TRUVADA group who was infected with wild type virus at enrollment selected an M184V expressing virus by Week 12. Two of the five subjects in the TDF group had tenofovir-resistant viruses at the time of seroconversion; one subject infected with wild type virus at enrollment developed a K65R substitution by Week 16, while the second subject had virus expressing the combination of D67N and K70R substitutions upon seroconversion at Week 60, although baseline virus was not genotyped and it is unclear if the resistance emerged or was transmitted. Following enrollment, 4 subjects (2 in the TDF group, 1 in the TRUVADA group, and 1 in the placebo group) had virus expressing K103N or V106A substitutions, which confer high-level resistance to NNRTIs but have not been associated with FTC or TDF and may have been present in the infecting virus.

ATN113 Trial: In ATN113, a clinical trial of HIV-1 seronegative adolescent subjects [see Use in Specific Populations (8.4)], no amino acid substitutions associated with resistance to FTC or TDF were detected at the time of seroconversion from any of the 3 subjects who became infected with HIV-1 during the trial. All 3 subjects who seroconverted were nonadherent to the recommended TRUVADA dosage.

Cross Resistance

Emtricitabine and Tenofovir Disoproxil Fumarate: Cross-resistance among certain NRTIs has been recognized. The M184V/I and/or K65R substitutions selected in cell culture by the combination of FTC and tenofovir are also observed in some HIV-1 isolates from subjects failing treatment with tenofovir in combination with either FTC or lamivudine, and either abacavir or didanosine. Therefore, cross-resistance among these drugs may occur in patients whose virus harbors either or both of these amino acid substitutions.

Emtricitabine: FTC-resistant isolates (M184V/I) were cross-resistant to lamivudine but retained susceptibility in cell culture to the NRTIs didanosine, stavudine, tenofovir, and zidovudine, and to NNRTIs (delavirdine, efavirenz, and nevirapine). HIV-1 isolates containing the K65R substitution, selected in vivo by abacavir, didanosine, and tenofovir, demonstrated reduced susceptibility to inhibition by FTC. Viruses harboring substitutions conferring reduced susceptibility to stavudine and zidovudine (M41L, D67N, K70R, L210W, T215Y/F, K219Q/E), or didanosine (L74V) remained sensitive to FTC. HIV-1 containing the K103N substitution associated with resistance to NNRTIs was susceptible to FTC.

Tenofovir Disoproxil Fumarate: The K65R and K70E substitutions selected by tenofovir are also selected in some HIV-1 infected patients treated with abacavir or didanosine. HIV-1 isolates with the K65R and K70E substitutions also showed reduced susceptibility to FTC and lamivudine. Therefore, cross-resistance among these NRTIs may occur in patients whose virus harbors the K65R or K70E substitutions. HIV-1 isolates from subjects (N=20) whose HIV-1 expressed a mean of 3 zidovudine-associated RT amino acid substitutions (M41L, D67N, K70R, L210W, T215Y/F, or K219Q/E/N) showed a 3.1-fold decrease in the susceptibility to tenofovir. Subjects whose virus expressed an L74V substitution without zidovudine resistance-associated substitutions (N=8) had reduced response to TDF. Limited data are available for patients whose virus expressed a Y115F substitution (N=3), Q151M substitution (N=2), or T69 insertion (N=4), all of whom had a reduced response.

13 NONCLINICAL TOXICOLOGY

13.1 Carcinogenesis, Mutagenesis, Impairment of Fertility

Emtricitabine: In long-term oral carcinogenicity studies of FTC, no drug-related increases in tumor incidence were found in mice at doses up to 750 mg/kg/day (26 times the human systemic exposure at the therapeutic dose of 200 mg/day) or in rats at doses up to 600 mg/kg/day (31 times the human systemic exposure at the therapeutic dose).

FTC was not genotoxic in the reverse mutation bacterial test (Ames test), or the mouse lymphoma or mouse micronucleus assays.

FTC did not affect fertility in male rats at approximately 140-fold or in male and female mice at approximately 60-fold higher exposures (AUC) than in humans given the recommended 200 mg daily dose. Fertility was normal in the offspring of mice exposed daily from before birth (in utero) through sexual maturity at daily exposures (AUC) of approximately 60-fold higher than human exposures at the recommended 200 mg daily dose.

Tenofovir Disoproxil Fumarate: Long-term oral carcinogenicity studies of TDF in mice and rats were carried out at exposures up to approximately 16 times (mice) and 5 times (rats) those observed in humans at the therapeutic dose for HIV-1 infection. At the high dose in female mice, liver adenomas were increased at exposures 16 times that in humans. In rats, the study was negative for carcinogenic findings at exposures up to 5 times that observed in humans at the therapeutic dose.

TDF was mutagenic in the in vitro mouse lymphoma assay and negative in an in vitro bacterial mutagenicity test (Ames test). In an in vivo mouse micronucleus assay, TDF was negative when administered to male mice.

There were no effects on fertility, mating performance, or early embryonic development when TDF was administered to male rats at a dose equivalent to 10 times the human dose based on body surface area comparisons for 28 days prior to mating and to female rats for 15 days prior to mating through day 7 of gestation. There was, however, an alteration of the estrous cycle in female rats.

13.2 Animal Toxicology and/or Pharmacology

Tenofovir and TDF administered in toxicology studies to rats, dogs, and monkeys at exposures (based on AUCs) greater than or equal to 6-fold those observed in humans caused bone toxicity. In monkeys the bone toxicity was diagnosed as osteomalacia. Osteomalacia observed in monkeys appeared to be reversible upon dose reduction or discontinuation of tenofovir. In rats and dogs, the bone toxicity manifested as reduced bone mineral density. The mechanism(s) underlying bone toxicity is unknown.

Evidence of renal toxicity was noted in four animal species. Increases in serum creatinine, BUN, glycosuria, proteinuria, phosphaturia, and/or calciuria and decreases in serum phosphate were observed to varying degrees in these animals. These toxicities were noted at exposures (based on AUCs) 2–20 times higher than those observed in humans. The relationship of the renal abnormalities, particularly the phosphaturia, to the bone toxicity is not known.

14 CLINICAL STUDIES

14.1 Overview of Clinical Trials

The efficacy and safety of TRUVADA have been evaluated in the studies summarized in Table 13.

Table 13 Trials Conducted with TRUVADA for HIV-1 Treatment and HIV-1 PrEP
Trial | Population | Study Arms (N) [Randomized and dosed.] | Timepoint
Study 934 [Randomized, open label, active-controlled trial.] (NCT00112047) | HIV-infected, treatment-naïve adults | FTC+TDF + efavirenz (257) zidovudine/lamivudine + efavirenz (254) | 48 Weeks
iPrEx [Randomized, double-blind, placebo-controlled trial.] (NCT00458393) | HIV-seronegative men or transgender women who have sex with men | TRUVADA (1,251) Placebo (1,248) | 4,237 person-years
Partners PrEP (NCT00557245) | HIV serodiscordant heterosexual couples | TRUVADA (1,583) Placebo (1,586) | 7,827 person-years

14.2 Clinical Trial Results for Treatment of HIV-1: Study 934

Data through 144 weeks are reported for Study 934, a randomized, open-label, active-controlled multicenter trial comparing FTC+TDF administered in combination with efavirenz (EFV) versus zidovudine (AZT)/lamivudine (3TC) fixed-dose combination administered in combination with EFV in 511 antiretroviral-naïve adult subjects. From Weeks 96 to 144 of the trial, subjects received TRUVADA with EFV in place of FTC+TDF with EFV. Subjects had a mean age of 38 years (range 18–80); 86% were male, 59% were Caucasian, and 23% were Black. The mean baseline CD4+ cell count was 245 cells/mm^3 (range 2–1,191) and median baseline plasma HIV-1 RNA was 5.01 log10 copies/mL (range 3.56–6.54). Subjects were stratified by baseline CD4+ cell count (< or ≥200 cells/mm^3); 41% had CD4+ cell counts <200 cells/mm^3 and 51% of subjects had baseline viral loads >100,000 copies/mL. Treatment outcomes through 48 and 144 weeks for those subjects who did not have EFV resistance at baseline are presented in Table 14.

Table 14 Virologic Outcomes of Randomized Treatment at Weeks 48 and 144 (Study 934)
Outcomes | At Week 48 |  | At Week 144
Outcomes | FTC+TDF +EFV (N=244) | AZT/3TC +EFV (N=243) | FTC+TDF +EFV (N=227) [Subjects who were responders at Week 48 or Week 96 (HIV-1 RNA <400 copies/mL) but did not consent to continue trial after Week 48 or Week 96 were excluded from analysis.] | AZT/3TC +EFV (N=229)
Responder [Subjects achieved and maintained confirmed HIV-1 RNA <400 copies/mL through Weeks 48 and 144.] | 84% | 73% | 71% | 58%
Virologic failure [Includes confirmed viral rebound and failure to achieve confirmed <400 copies/mL through Weeks 48 and 144.] | 2% | 4% | 3% | 6%
Rebound | 1% | 3% | 2% | 5%
Never suppressed | 0% | 0% | 0% | 0%
Change in antiretroviral regimen | 1% | 1% | 1% | 1%
Death | <1% | 1% | 1% | 1%
Discontinued due to adverse event | 4% | 9% | 5% | 12%
Discontinued for other reasons [Includes lost to follow-up, subject withdrawal, noncompliance, protocol violation, and other reasons.] | 10% | 14% | 20% | 22%

Through Week 48, 84% and 73% of subjects in the FTC+TDF group and the AZT/3TC group, respectively, achieved and maintained HIV-1 RNA <400 copies/mL (71% and 58% through Week 144). The difference in the proportion of subjects who achieved and maintained HIV-1 RNA <400 copies/mL through 48 weeks is largely due to the higher number of discontinuations due to adverse events and other reasons in the AZT/3TC group in this open-label trial. In addition, 80% and 70% of subjects in the FTC+TDF group and the AZT/3TC group, respectively, achieved and maintained HIV-1 RNA <50 copies/mL through Week 48 (64% and 56% through Week 144). The mean increase from baseline in CD4+ cell count was 190 cells/mm^3 in the FTC+TDF group and 158 cells/mm^3 in the AZT/3TC group at Week 48 (312 and 271 cells/mm^3 at Week 144).

Through 48 weeks, 7 subjects in the FTC+TDF group and 5 subjects in the AZT/3TC group experienced a new CDC Class C event (10 and 6 subjects through 144 weeks).

14.3 Clinical Trial Results for HIV-1 PrEP: iPrEx

The iPrEx trial was a randomized, double-blind, placebo-controlled multinational study evaluating TRUVADA in 2,499 HIV-seronegative men or transgender women who have sex with men and with evidence of high-risk behavior for HIV-1 infection. Evidence of high-risk behavior included any one of the following reported to have occurred up to six months prior to study screening: no condom use during anal intercourse with an HIV-1 positive partner or a partner of unknown HIV status; anal intercourse with more than 3 sex partners; exchange of money, gifts, shelter, or drugs for anal sex; sex with male partner and diagnosis of sexually transmitted infection; no consistent use of condoms with sex partner known to be HIV-1 positive.

All subjects received monthly HIV-1 testing, risk-reduction counseling, condoms, and management of sexually transmitted infections. Of the 2,499 enrolled subjects, 1,251 received TRUVADA and 1,248 received placebo. The mean age of subjects was 27 years; 5% were Asian, 9% Black, 18% White, and 72% Hispanic/Latino.

Subjects were followed for 4,237 person-years. The primary outcome measure was the incidence of documented HIV seroconversion. At the end of treatment, emergent HIV-1 seroconversion was observed in 131 subjects, of which 48 occurred in the TRUVADA group and 83 occurred in the placebo group, indicating a 42% (95% CI: 18–60%) reduction in risk. Risk reduction was found to be higher (53%; 95% CI: 34–72%) among subjects who reported previous unprotected anal intercourse (URAI) at screening (732 and 753 subjects reported URAI within the last 12 weeks at screening in the TRUVADA and placebo groups, respectively). In a post-hoc case control study of plasma and intracellular drug levels in about 10% of study subjects, risk reduction appeared to be greatest in subjects with detectable intracellular tenofovir diphosphate concentrations. Efficacy was therefore strongly correlated with adherence.

14.4 Clinical Trial Results for HIV-1 PrEP: Partners PrEP

The Partners PrEP trial was a randomized, double-blind, placebo-controlled 3-arm trial conducted in 4,758 HIV-1 serodiscordant heterosexual couples in Kenya and Uganda to evaluate the efficacy and safety of TDF (N=1,589) and FTC/TDF (N=1,583) versus (parallel comparison) placebo (N=1,586) in preventing HIV-1 acquisition by the uninfected partner.

All uninfected partner subjects received monthly HIV-1 testing, evaluation of adherence, assessment of sexual behavior, and safety evaluations. Women were also tested monthly for pregnancy. Women who became pregnant during the trial had study drug interrupted for the duration of the pregnancy and while breastfeeding. The uninfected partner subjects were predominantly male (61–64% across study drug groups) and had a mean age of 33–34 years.

Following 7,827 person-years of follow-up, 82 emergent HIV-1 seroconversions were reported, with an overall observed seroincidence rate of 1.05 per 100 person-years. Of the 82 seroconversions, 13 and 52 occurred in partner subjects randomized to TRUVADA and placebo, respectively. Two of the 13 seroconversions in the TRUVADA arm and 3 of the 52 seroconversions in the placebo arm occurred in women during treatment interruptions for pregnancy. The risk reduction for TRUVADA relative to placebo was 75% (95% CI: 55–87%). In a post-hoc case control study of plasma drug levels in about 10% of study subjects, risk reduction appeared to be greatest in subjects with detectable plasma tenofovir concentrations. Efficacy was therefore strongly correlated with adherence.

16 HOW SUPPLIED/STORAGE AND HANDLING

TRUVADA tablets are available in bottles containing 30 tablets with child-resistant closure as follows:

- 100 mg of FTC and 150 mg of TDF (equivalent to 123 mg of tenofovir disoproxil) tablets are blue, oval shaped, film coated, debossed with "GSI" on one side and with "703" on the other side (NDC 61958-0703-1).
- 133 mg of FTC and 200 mg of TDF (equivalent to 163 mg of tenofovir disoproxil) tablets are blue, rectangular shaped, film coated, debossed with "GSI" on one side and with "704" on the other side (NDC 61958-0704-1).
- 167 mg of FTC and 250 mg of TDF (equivalent to 204 mg of tenofovir disoproxil) tablets are blue, modified capsule shaped, film coated, debossed with "GSI" on one side and with "705" on the other side (NDC 61958-0705-1).
- 200 mg of FTC and 300 mg of TDF (equivalent to 245 mg of tenofovir disoproxil) tablets are blue, capsule shaped, film coated, debossed with "GILEAD" on one side and with "701" on the other side (NDC 61958-0701-1).

STORAGE AND HANDLING

Store at 25 °C (77 °F), excursions permitted to 15 °C–30 °C (59 °F–86 °F) (see USP Controlled Room Temperature).

- Keep container tightly closed.
- Dispense only in original container.

17 PATIENT COUNSELING INFORMATION

Advise the patient to read the FDA-approved patient labeling (Medication Guide).

Important Information for Uninfected Individuals Taking TRUVADA for HIV-1 PrEP

Advise HIV-uninfected individuals about the following [see Warnings and Precautions (5.2)]:

- The need to confirm that they are HIV-negative before starting to take TRUVADA to reduce the risk of acquiring HIV-1.
- That HIV-1 resistance substitutions may emerge in individuals with undetected HIV-1 infection who are taking TRUVADA, because TRUVADA alone does not constitute a complete regimen for HIV-1 treatment.
- The importance of taking TRUVADA on a regular dosing schedule and strict adherence to the recommended dosing schedule to reduce the risk of acquiring HIV-1. Uninfected individuals who miss doses are at greater risk of acquiring HIV-1 than those who do not miss doses.
- That TRUVADA does not prevent other sexually acquired infections and should only be used as part of a complete prevention strategy including other prevention measures.
- To use condoms consistently and correctly to lower the chances of sexual contact with any body fluids such as semen, vaginal secretions, or blood.
- The importance of knowing their HIV-1 status and the HIV-1 status of their partner(s).
- The importance of virologic suppression in their partner(s) with HIV-1.
- The need to get tested regularly for HIV-1 (at least every 3 months, or more frequently for some individuals such as adolescents) and to ask their partner(s) to get tested as well.
- To report any symptoms of acute HIV-1 infection (flu-like symptoms) to their healthcare provider immediately.
- That the signs and symptoms of acute infection include fever, headache, fatigue, arthralgia, vomiting, myalgia, diarrhea, pharyngitis, rash, night sweats, and adenopathy (cervical and inguinal).
- To get tested for other sexually transmitted infections, such as syphilis, chlamydia, and gonorrhea, that may facilitate HIV-1 transmission.
- To assess their sexual risk behavior and get support to help reduce sexual risk behavior.

Severe Acute Exacerbation of Hepatitis B in Patients Infected with HBV

Inform individuals that severe acute exacerbations of hepatitis B have been reported in patients who are infected with HBV and have discontinued TRUVADA [see Warnings and Precautions (5.1)]. Advise HBV-infected individuals to not discontinue TRUVADA without first informing their healthcare provider.

New Onset or Worsening Renal Impairment

Inform HIV-1 infected patients and uninfected individuals that renal impairment, including cases of acute renal failure and Fanconi syndrome, has been reported in association with the use of TDF, a component of TRUVADA. Advise patients to avoid TRUVADA with concurrent or recent use of a nephrotoxic agent (e.g., high-dose or multiple NSAIDs) [see Warnings and Precautions (5.3)]. The dosing interval of TRUVADA may need adjustment in HIV-1 infected patients with renal impairment. TRUVADA for HIV-1 PrEP should not be used in HIV-1 uninfected individuals if estimated creatinine clearance is less than 60 mL/min. If a decrease in estimated creatinine clearance is observed in uninfected individuals while using TRUVADA for HIV-1 PrEP, evaluate potential causes and re-assess potential risks and benefits of continued use [see Dosage and Administration (2.6)].

Immune Reconstitution Syndrome

Inform HIV-1 infected patients that in some patients with advanced HIV infection (AIDS), signs and symptoms of inflammation from previous infections may occur soon after anti-HIV treatment is started. It is believed that these symptoms are due to an improvement in the body's immune response, enabling the body to fight infections that may have been present with no obvious symptoms. Advise patients to inform their healthcare provider immediately of any symptoms of infection [see Warnings and Precautions (5.4)].

Bone Loss and Mineralization Defects

Inform patients that decreases in bone mineral density have been observed with the use of TDF or TRUVADA. Consider bone monitoring in patients and uninfected individuals who have a history of pathologic bone fracture or at risk for osteopenia [see Warnings and Precautions (5.5)].

Lactic Acidosis and Severe Hepatomegaly

Inform HIV-1 infected patients and uninfected individuals that lactic acidosis and severe hepatomegaly with steatosis, including fatal cases, have been reported. Treatment with TRUVADA should be suspended in any person who develops clinical symptoms suggestive of lactic acidosis or pronounced hepatotoxicity [see Warnings and Precautions (5.6)].

Drug Interactions

Advise individuals that TRUVADA may interact with many drugs; therefore, advise individuals to report to their healthcare provider the use of any other medication, including other HIV drugs and drugs for treatment of hepatitis C virus [see Warnings and Precautions (5.7) and Drug Interactions (7)].

Dosage Recommendations for Treatment of HIV-1 Infection

Inform HIV-1 infected patients that it is important to take TRUVADA with other antiretroviral drugs for the treatment of HIV-1 on a regular dosing schedule with or without food and to avoid missing doses as it can result in development of resistance.

Pregnancy Registry

Inform individuals using TRUVADA for HIV-1 treatment or HIV-1 PrEP that there is an antiretroviral pregnancy registry to monitor fetal outcomes of pregnant women exposed to TRUVADA [see Use in Specific Populations (8.1)].

Lactation

Instruct mothers not to breastfeed if they are taking TRUVADA for the treatment of HIV-1 infection or if acute HIV-1 infection is suspected in a mother taking TRUVADA for HIV-1 PrEP because of the risk of passing the HIV-1 virus to the baby. In HIV-uninfected women, the benefits and risks of TRUVADA while breastfeeding should be evaluated, including the risk of HIV-1 acquisition due to medication nonadherence and subsequent mother to child transmission [see Use in Specific Populations (8.2)].

TRUVADA, ATRIPLA, COMPLERA, EMTRIVA, EPCLUSA, HARVONI, SOVALDI, STRIBILD, and VIREAD are trademarks of Gilead Sciences, Inc., or its related companies. All other trademarks referenced herein are the property of their respective owners.

© 2024 Gilead Sciences, Inc. All rights reserved.

Manufactured for and distributed by:

Gilead Sciences, Inc.
Foster City, CA 94404

21752-GS-035

Medication Guide
TRUVADA® (tru-VAH-dah)
(emtricitabine and tenofovir disoproxil fumarate)
tablets

Read this Medication Guide before you start taking TRUVADA and each time you get a refill. There may be new information. This information does not take the place of talking to your healthcare provider about your medical condition or your treatment.
This Medication Guide provides information about two different ways that TRUVADA may be used. See the section "What is TRUVADA?" for detailed information about how TRUVADA may be used.

What is the most important information I should know about TRUVADA?
TRUVADA can cause serious side effects, including:

- Worsening of hepatitis B virus infection (HBV). Your healthcare provider will test you for HBV before start or when you start treatment with TRUVADA. If you have HBV infection and take TRUVADA, your HBV may get worse (flare-up) if you stop taking TRUVADA. A "flare-up" is when your HBV infection suddenly returns in a worse way than before.
  - Do not run out of TRUVADA. Refill your prescription or talk to your healthcare provider before your TRUVADA is all gone.
  - Do not stop taking TRUVADA without first talking to your healthcare provider.
  - If you stop taking TRUVADA, your healthcare provider will need to check your health often and do blood tests regularly for several months to check your HBV infection, or give you a medicine to treat hepatitis B. Tell your healthcare provider about any new or unusual symptoms you may have after you stop taking TRUVADA.

For more information about side effects, see the section "What are the possible side effects of TRUVADA?".
Other important information for people who take TRUVADA to help reduce their risk of getting human immunodeficiency virus-1 (HIV-1) infection, also called pre-exposure prophylaxis or "PrEP":
Before taking TRUVADA to reduce your risk of getting HIV-1:

- You must be HIV-1 negative to start TRUVADA. You must get tested to make sure that you do not already have HIV-1 infection.
- Do not take TRUVADA for HIV-1 PrEP unless you are confirmed to be HIV-1 negative.
- Some HIV-1 tests can miss HIV-1 infection in a person who has recently become infected. If you have flu-like symptoms, you could have recently become infected with HIV-1. Tell your healthcare provider if you had a flu-like illness within the last month before starting TRUVADA or at any time while taking TRUVADA. Symptoms of new HIV-1 infection include:

- tiredness
- fever
- joint or muscle aches
- headache
- sore throat

- vomiting or diarrhea
- rash
- night sweats
- enlarged lymph nodes in the neck or groin

While you are taking TRUVADA for HIV-1 PrEP:

- TRUVADA does not prevent other sexually transmitted infections (STIs). Practice safer sex by using a latex or polyurethane condom to reduce the risk of getting STIs.
- You must stay HIV-negative to keep taking TRUVADA for HIV-1 PrEP.
  - Know your HIV-1 status and the HIV-1 status of your partners.
  - Ask your partners with HIV-1 if they are taking anti-HIV-1 medicines and have an undetectable viral load. An undetectable viral load is when the amount of virus in the blood is too low to be measured in a lab test. To maintain an undetectable viral load, your partners must keep taking HIV-1 medicines every day. Your risk of getting HIV-1 is lower if your partners with HIV-1 are taking effective treatment.
  - Get tested for HIV-1 at least every 3 months or when your healthcare provider tells you.
  - Get tested for other STIs such as syphilis, chlamydia, and gonorrhea. These infections make it easier for HIV-1 to infect you.
  - If you think you were exposed to HIV-1, tell your healthcare provider right away. They may want to do more tests to be sure you are still HIV-1 negative.
  - Get information and support to help reduce sexual risk behaviors.
  - Do not miss any doses of TRUVADA. Missing doses increases your risk of getting HIV-1 infection.
- If you do become HIV-1 positive, you need more medicine than TRUVADA alone to treat HIV-1. TRUVADA by itself is not a complete treatment for HIV-1.

If you have HIV-1 and take only TRUVADA, over time your HIV-1 may become harder to treat.

What is TRUVADA?
TRUVADA is a prescription medicine that may be used in two different ways. TRUVADA is used:

- to treat HIV-1 infection when used with other anti-HIV-1 medicines in adults and children who weigh at least 37 pounds (at least 17 kg).
- for HIV-1 PrEP to reduce the risk of getting HIV-1 infection in adults and adolescents who weigh at least 77 pounds (at least 35 kg).

HIV-1 is the virus that causes Acquired Immune Deficiency Syndrome (AIDS).
TRUVADA contains the prescription medicines emtricitabine and tenofovir disoproxil fumarate.
It is not known if TRUVADA for treatment of HIV-1 infection is safe and effective in children who weigh less than 37 pounds (17 kg).
It is not known if TRUVADA is safe and effective in reducing the risk of HIV-1 infection in people who weigh less than 77 pounds (35 kg).

For people taking TRUVADA for HIV-1 PrEP:
Do not take TRUVADA for HIV-1 PrEP if:

- you already have HIV-1 infection. If you are HIV-1 positive, you need to take other medicines with TRUVADA to treat HIV-1. TRUVADA by itself is not a complete treatment for HIV-1.
- you do not know your HIV-1 infection status. You may already be HIV-1 positive. You need to take other HIV-1 medicines with TRUVADA to treat HIV-1.

TRUVADA can only help reduce your risk of getting HIV-1 before you are infected.

What should I tell my healthcare provider before taking TRUVADA?
Before taking TRUVADA, tell your healthcare provider about all of your medical conditions, including if you:

- have liver problems, including HBV infection
- have kidney problems or receive kidney dialysis treatment
- have bone problems
- are pregnant or plan to become pregnant. It is not known if TRUVADA can harm your unborn baby. Tell your healthcare provider if you become pregnant during treatment with TRUVADA.
  Pregnancy Registry: There is a pregnancy registry for people who take TRUVADA during pregnancy. The purpose of this registry is to collect information about the health of you and your baby. Talk with your healthcare provider about how you can take part in this registry.
- are breastfeeding or plan to breastfeed. TRUVADA can pass to your baby in your breast milk.
  - Do not breastfeed if you have HIV-1 or if you think you have recently become infected with HIV-1 because of the risk of passing HIV-1 to your baby.
  - If you take TRUVADA for HIV-1 PrEP, talk with your healthcare provider about the best way to feed your baby.

Tell your healthcare provider about all the medicines you take, including prescription and over-the-counter medicines, vitamins, and herbal supplements.
Some medicines may interact with TRUVADA. Keep a list of your medicines and show it to your healthcare provider and pharmacist when you get a new medicine.

- You can ask your healthcare provider or pharmacist for a list of medicines that interact with TRUVADA.
- Do not start a new medicine without telling your healthcare provider. Your healthcare provider can tell you if it is safe to take TRUVADA with other medicines.

How should I take TRUVADA?

- Take TRUVADA exactly as your healthcare provider tells you to take it. If you take TRUVADA to treat HIV-1 infection, you need to take other HIV-1 medicines. Your healthcare provider will tell you what medicines to take and how to take them.
- Take TRUVADA 1 time each day with or without food.
- Children who take TRUVADA are prescribed a lower strength tablet than adults. Children should swallow the TRUVADA tablet. Tell your healthcare provider if your child cannot swallow the tablet, because they may need a different HIV-1 medicine.
  - Your healthcare provider will change the dose of TRUVADA as needed based on your child's weight.
- Do not change your dose or stop taking TRUVADA without first talking with your healthcare provider. Stay under a healthcare provider's care when taking TRUVADA. Do not miss a dose of TRUVADA.
- If you take too much TRUVADA, call your healthcare provider or go to the nearest hospital emergency room right away.
- When your TRUVADA supply starts to run low, get more from your healthcare provider or pharmacy.
  - If you are taking TRUVADA for treatment of HIV-1, the amount of virus in your blood may increase if the medicine is stopped for even a short time. The virus may develop resistance to TRUVADA and become harder to treat.
  - If you are taking TRUVADA for HIV-1 PrEP, missing doses increases your risk of getting HIV-1 infection.

What are the possible side effects of TRUVADA?
TRUVADA may cause serious side effects, including:

- See "What is the most important information I should know about TRUVADA?"
- New or worse kidney problems, including kidney failure. Your healthcare provider should do blood and urine tests to check your kidneys before you start and during treatment with TRUVADA. Your healthcare provider may tell you to take TRUVADA less often, or to stop taking TRUVADA if you get new or worse kidney problems.
- Changes in your immune system (Immune Reconstitution Syndrome) can happen when taking medicines to treat HIV-1 infection. Your immune system may get stronger and begin to fight infections that have been hidden in your body for a long time. Tell your healthcare provider right away if you start having any new symptoms after starting your HIV-1 medicine.
- Bone problems can happen in some people who take TRUVADA. Bone problems include bone pain, or softening or thinning of bones, which may lead to fractures. Your healthcare provider may need to do tests to check your bones.
- Too much lactic acid in your blood (lactic acidosis). Too much lactic acid is a serious but rare medical emergency that can lead to death. Tell your healthcare provider right away if you get these symptoms: weakness or being more tired than usual, unusual muscle pain, being short of breath or fast breathing, stomach pain with nausea and vomiting, cold or blue hands and feet, feel dizzy or lightheaded, or a fast or abnormal heartbeat.
- Severe liver problems. In rare cases, severe liver problems can happen that can lead to death. Tell your healthcare provider right away if you get these symptoms: skin or the white part of your eyes turns yellow, dark "tea-colored" urine, light-colored stools, loss of appetite for several days or longer, nausea, or stomach-area pain.

The most common side effects of TRUVADA for treatment of HIV-1 include:

- diarrhea
- nausea
- tiredness
- headache
- dizziness

- depression
- problems sleeping
- abnormal dreams
- rash

Common side effects in people who take TRUVADA for HIV-1 PrEP include:

- headache

- stomach-area (abdomen) pain

- decreased weight

These are not all the possible side effects of TRUVADA.
Call your doctor for medical advice about side effects. You may report side effects to FDA at 1-800-FDA-1088.

How should I store TRUVADA?

- Store TRUVADA at room temperature between 68°F to 77°F (20°C to 25°C).
- Keep TRUVADA in its original container.
- Keep the container tightly closed.
- Do not use TRUVADA if seal over bottle opening is broken or missing.

Keep TRUVADA and all other medicines out of reach of children.

General information about TRUVADA.
Medicines are sometimes prescribed for purposes other than those listed in a Medication Guide. Do not use TRUVADA for a condition for which it was not prescribed. Do not give TRUVADA to other people, even if they have the same symptoms you have. It may harm them. You can ask your healthcare provider or pharmacist for information about TRUVADA that is written for health professionals.

What are the ingredients in TRUVADA?
Active ingredients: emtricitabine and tenofovir disoproxil fumarate.
Inactive ingredients: croscarmellose sodium, lactose monohydrate, magnesium stearate, microcrystalline cellulose, and pregelatinized starch (gluten free). The 200 mg/300 mg strength tablets are coated with Opadry II Blue Y-30-10701, which contains FD&C Blue #2 aluminum lake, hypromellose 2910, lactose monohydrate, titanium dioxide, and triacetin. The 167 mg/250 mg, 133 mg/200 mg, and 100 mg/150 mg strength tablets are coated with Opadry II Blue, which contains FD&C Blue #2 aluminum lake, hypromellose 2910, lactose monohydrate, titanium dioxide, and triacetin.
Manufactured for and distributed by:
Gilead Sciences, Inc.
Foster City, CA 94404
TRUVADA is a trademark of Gilead Sciences, Inc., or its related companies.
© 2024 Gilead Sciences, Inc. All rights reserved.
21752-GS-035
For more information, call 1-800-445-3235 or go to www.TRUVADA.com.

This Medication Guide has been approved by the U.S. Food and Drug Administration.

Revised: 04/2024

PRINCIPAL DISPLAY PANEL - 200 mg/300 mg Tablet Bottle Label

NDC 61958-0701-1

Truvada®
(emtricitabine and
tenofovir disoproxil
fumarate) tablets

200 mg / 300 mg

30 tablets
Rx only

DISPENSER: Each time Truvada is dispensed
give the patient the attached Medication Guide.

PRINCIPAL DISPLAY PANEL - 100 mg/150 mg Tablet Bottle Label

NDC 61958-0703-1

Truvada®
(emtricitabine and
tenofovir disoproxil
fumarate) tablets

100 mg/150 mg

30 tablets
Rx only

DISPENSER: Each time Truvada is dispensed
give the patient the attached Medication Guide.

PRINCIPAL DISPLAY PANEL - 133 mg/200 mg Tablet Bottle Label

NDC 61958-0704-1

Truvada®
(emtricitabine and
tenofovir disoproxil
fumarate) tablets

133 mg/200 mg

30 tablets
Rx only

DISPENSER: Each time Truvada is dispensed
give the patient the attached Medication Guide.

PRINCIPAL DISPLAY PANEL - 167 mg/250 mg Tablet Bottle Label

NDC 61958-0705-1

Truvada®
(emtricitabine and
tenofovir disoproxil
fumarate) tablets

167 mg/250 mg

30 tablets
Rx only

DISPENSER: Each time Truvada is dispensed
give the patient the attached Medication Guide.